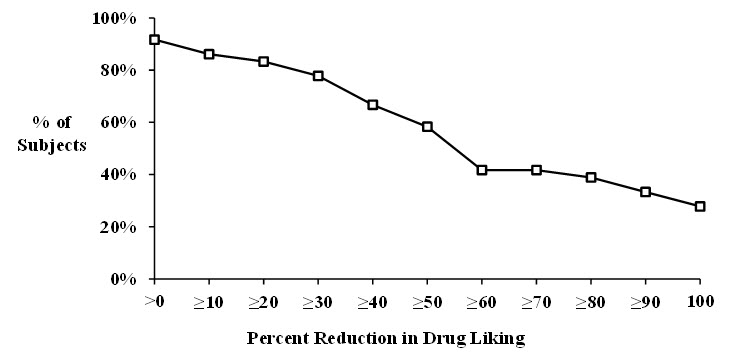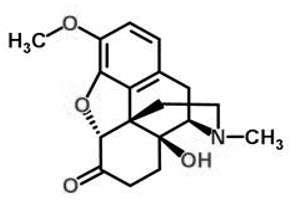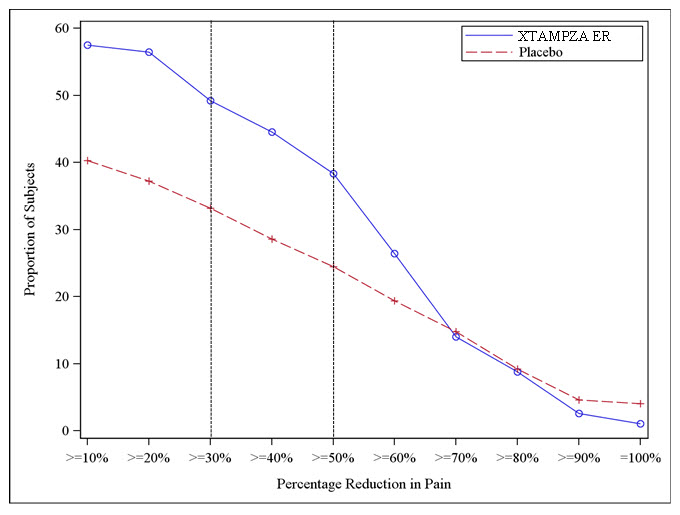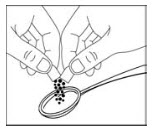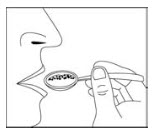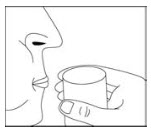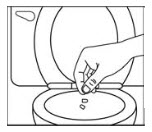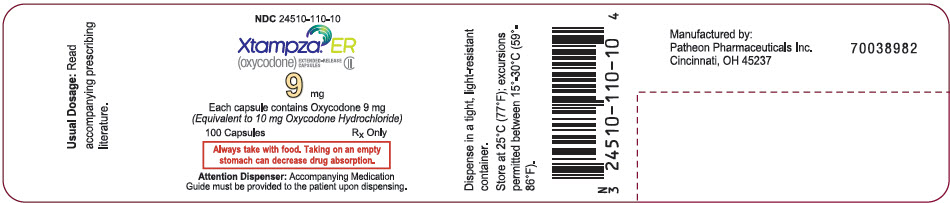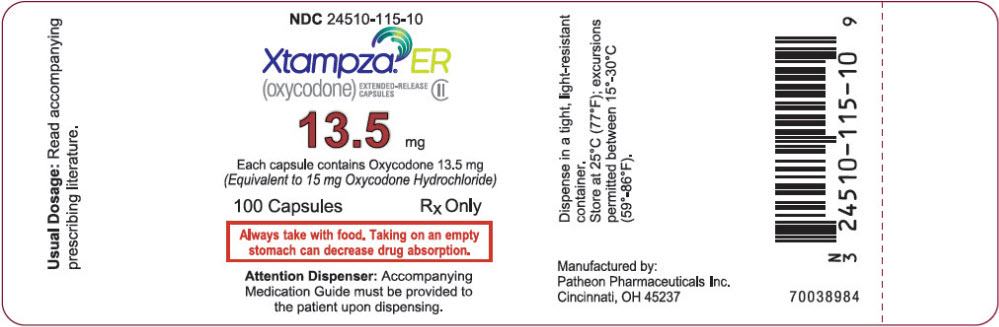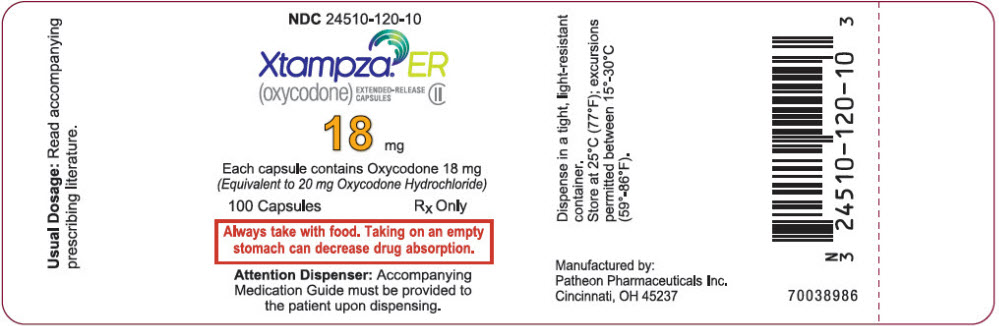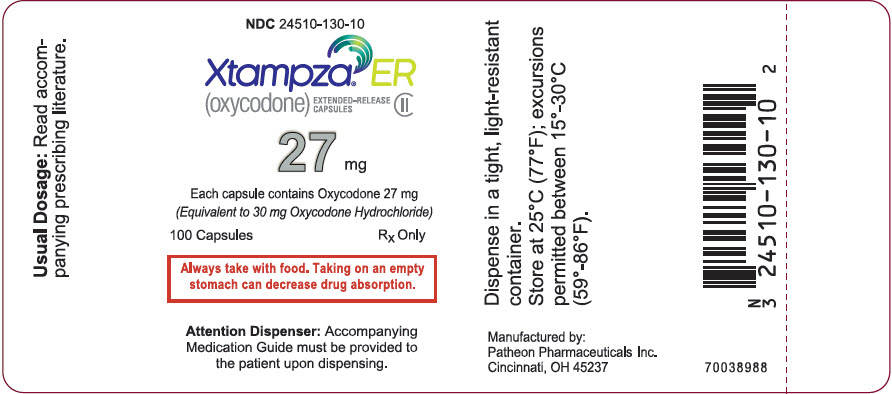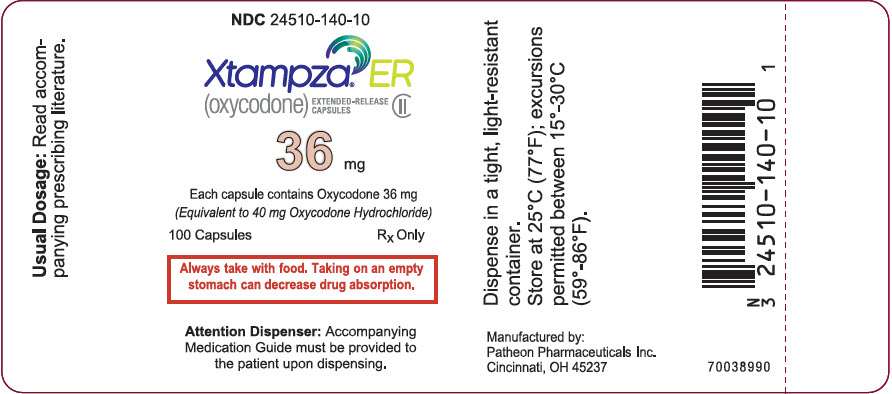 DRUG LABEL: XTAMPZA 
NDC: 24510-110 | Form: CAPSULE, EXTENDED RELEASE
Manufacturer: Collegium Pharmaceutical, Inc.
Category: prescription | Type: HUMAN PRESCRIPTION DRUG LABEL
Date: 20251230
DEA Schedule: CII

ACTIVE INGREDIENTS: OXYCODONE 9 mg/1 1
INACTIVE INGREDIENTS: MYRISTIC ACID; YELLOW WAX; CARNAUBA WAX; PEG-32 STEARATE; MAGNESIUM STEARATE; SILICON DIOXIDE; HYPROMELLOSE, UNSPECIFIED; TITANIUM DIOXIDE; WATER; FERRIC OXIDE YELLOW

HIGHLIGHTS OF PRESCRIBING INFORMATION

These highlights do not include all the information needed to use XTAMPZA® ER safely and effectively. See full prescribing information for XTAMPZA ER.
XTAMPZA ER (oxycodone) extended-release capsules, for oral use, CII
Initial U.S. Approval: 1950

WARNING: SERIOUS AND LIFE-THREATENING RISKS FROM USE OF XTAMPZA ER

See full prescribing information for complete boxed warning.

- XTAMPZA ER exposes users to risks of addiction, abuse, and misuse, which can lead to overdose and death. Assess each patient's risk before prescribing and reassess regularly for these behaviors and conditions. (5.1)
- Serious, life-threatening, or fatal respiratory depression may occur especially during initiation or following a dosage increase. To reduce the risk of respiratory depression, proper dosing and titration of XTAMPZA ER are essential. (5.2)
- Accidental ingestion of XTAMPZA ER, especially by children, can result in fatal overdose of oxycodone. (5.2)
- Concomitant use of opioids with benzodiazepines or other central nervous system (CNS) depressants, including alcohol, may result in profound sedation, respiratory depression, coma, and death. Reserve concomitant prescribing for use in patients for whom alternative treatment options are inadequate. (5.3, 7)
- Advise pregnant using opioids for an extended period of time of the risk of Neonatal Opioid Withdrawal Syndrome, which may be life-threatening if not recognized and treated. Ensure that management by neonatology experts will be available at delivery. (5.4)
- Healthcare providers are strongly encouraged to complete a REMS-compliant education program and to counsel patients and caregivers on serious risks, safe use, and the importance of reading the Medication Guide with each prescription. (5.5)
- Concomitant use with CYP3A4 inhibitors (or discontinuation of CYP3A4 inducers) can result in a fatal overdose of oxycodone from XTAMPZA ER. (5.6, 12.3)

RECENT MAJOR CHANGES

Boxed Warning | 12/2025
Indications and Usage (1) | 12/2025
Dosage and Administration (2.1, 2.3, 2.5) | 12/2025
Warnings and Precautions (5.1, 5.2, 5.3, 5.14) | 12/2025

1 INDICATIONS AND USAGE

XTAMPZA ER is an opioid agonist indicated for the management of severe and persistent pain that requires an opioid analgesic and that cannot be adequately treated with alternative options, including immediate-release opioids. (1)

Limitations of Use

- Because of the risks of addiction, abuse, misuse, overdose, and death,which can occur at any dosage or duration and persist over the course of therapy, reserve opioid analgesics, including XTAMPZA ER, for use in patients for whom alternative treatment optionsare ineffective, not tolerated, or would be otherwise inadequate to provide sufficient management of pain. (1, 5.1)
- XTAMPZA ER is not indicated as an as-needed (prn) analgesic. (1)

2 DOSAGE AND ADMINISTRATION

- XTAMPZA ER should be prescribed only by healthcare professionals who are knowledgeable about the use of extended-release/long-acting opioids and how to mitigate the associated risks. (2.1)
- XTAMPZA ER at a total daily dose greater than 72 mg (equivalent to 80 mg oxycodone hydrochloride [HCl]) or a single dose greater than 36 mg (equivalent to 40 mg oxycodone HCl) is only for use in patients in whom tolerance to an opioid of comparable potency has been established. (2.1)
- Patients considered opioid-tolerant are those receiving, for one week or longer, at least 60 mg oral morphine per day, 25 mcg transdermal fentanyl per hour, 30 mg oral oxycodone HCl per day, 8 mg oral hydromorphone per day, 25 mg oral oxymorphone per day, 60 mg oral hydrocodone per day, or an equianalgesic dose of another opioid. (2.1)
- Use the lowest effective dose for the shortest duration of time consistent with individual patient treatment goals. Reserve titration to higher doses of XTAMPZA ER for patients in whom lower doses are insufficiently effective and in whom the expected benefits of using a higher dose opioid clearly outweigh the substantial risks. (2, 5)
- Initiate the dosing regimen for each patient individually, taking into account the patient's underlying cause and severity of pain, prior analgesic treatment and response, and risk factors for addiction, abuse, and misuse. (2.1, 5.1).
- Respiratory depression can occur at any time during opioid therapy, especially when initiating and following dosage increases with XTAMPZA ER. Consider this risk when selecting an initial dose and when making dose adjustments. (2.1, 5.2)
- Discuss opioid overdose reversal agents and options for acquiring them with the patient and/or caregiver, both when initiating and renewing treatment with XTAMPZA ER, especially if the patient has additional risk factors for overdose, or close contacts at risk for exposure and overdose. (2.2, 5.1, 5.2, 5.3)
- XTAMPZA ER is administered, twice daily, every 12 hours, and must be taken with food. Instruct patients to take XTAMPZA ER capsules with approximately the same amount of food for every dose to ensure consistent plasma levels are achieved. (2.1, 2.3)
- For patients who are not opioid tolerant, initiate with 9 mg (equivalent to 10 mg oxycodone HCl per day). (2.3)
- The daily dose of XTAMPZA ER must be limited to a maximum of 288 mg per day (equivalent to 320 mg oxycodone HCl per day). (2.1)
- Hepatic impairment: Initiate therapy at 1/3 to 1/2 the usual dosage and titrate carefully. Regularly evaluate. Use alternate analgesia for patients requiring less than 9 mg. (2.4, 8.6)
- Periodically reassess patients receiving XTAMPZA ER to evaluate the continued need for opioid analgesics to maintain pain control, for the signs or symptoms of adverse reactions, and for the development of addiction, abuse, or misuse. (2.5)
- Do not rapidly reduce or abruptly discontinue XTAMPZA ER in a physically-dependent patient because rapid reduction or abrupt discontinuation of opioid analgesics has resulted in serious withdrawal symptoms, uncontrolled pain, and suicide. (2.6, 5.14)
- Instruct patients to take XTAMPZA ER capsules with food in order to ensure consistent plasma levels are achieved. For patients who have difficulty swallowing, XTAMPZA ER can also be taken by sprinkling the capsule contents on soft foods or into a cup and then administering directly into the mouth, or through a gastrostomy or nasogastric feeding tube. (2.7)

3 DOSAGE FORMS AND STRENGTHS

Extended-release capsules:

- 9 mg (equivalent to 10 mg oxycodone HCl)
- 13.5 mg (equivalent to 15 mg oxycodone HCl)
- 18 mg (equivalent to 20 mg oxycodone HCl)
- 27 mg (equivalent to 30 mg oxycodone HCl)
- 36 mg (equivalent to 40 mg oxycodone HCl). (3)

4 CONTRAINDICATIONS

- Significant respiratory depression (4)
- Acute or severe bronchial asthma in an unmonitored setting or in absence of resuscitative equipment (4)
- Known or suspected gastrointestinal obstruction, including paralytic ileus (4)
- Hypersensitivity to oxycodone (4)

5 WARNINGS AND PRECAUTIONS

- Opioid-Induced Hyperalgesia and Allodynia: Opioid-Induced Hyperalgesia (OIH) occurs when an opioid analgesic paradoxically causes an increase in pain, or an increase in sensitivity to pain. If OIH is suspected, carefully consider appropriately decreasing the dose of the current opioid analgesic or opioid rotation. (5.7)
- Risk of life-threatening respiratory depression in patients with chronic pulmonary disease or in elderly, cachectic, or debilitated patients: Regularly evaluate. (5.8)
- Adrenal Insufficiency: If diagnosed, treat with physiologic replacement of corticosteroids, and wean patient off of the opioid. (5.9)
- Severe hypotension: Regularly evaluate. Avoid use of XTAMPZA ER in patients with circulatory shock. (5.10)
- Risks of use in patients with increased intracranial pressure, brain tumors, head injury, or impaired consciousness: Monitor for sedation and respiratory depression. Avoid use of XTAMPZA ER in patients with impaired consciousness or coma. (5.11)

6 ADVERSE REACTIONS

Most common adverse reactions (>5%) were nausea, headache, constipation, somnolence, pruritus, vomiting, and dizziness. (6.1).

To report SUSPECTED ADVERSE REACTIONS, contact Collegium Pharmaceutical, Inc. at 1-855-331-5615 or FDA at 1-800-FDA-1088 or www.fda.gov/medwatch.

7 DRUG INTERACTIONS

- CNS depressants: Concomitant use may cause profound sedation, respiratory depression, coma, and death. If coadministration is required, consider dose reduction of one or both drugs because of additive pharmacological effects and frequently evaluate. (5.3, 7)
- Serotonergic Drugs: Concomitant use may result in serotonin syndrome. Discontinue XTAMPZA ER if serotonin syndrome is suspected. (7)
- Mixed agonist/antagonist and partial agonist opioid analgesics: Avoid use with XTAMPZA ER because they may reduce analgesic effect of XTAMPZA ER or precipitate withdrawal symptoms. (7)
- Monoamine Oxidase Inhibitors (MAOIs): Can potentiate the effects of oxycodone. Avoid concomitant use in patients receiving MAOIs or within 14 days of stopping treatment with an MAOI. (7)

8 USE IN SPECIFIC POPULATIONS

- Pregnancy: May cause fetal harm. (8.1)
- Lactation: Not recommended. (8.2)

FULL PRESCRIBING INFORMATION

WARNING: SERIOUS AND LIFE-THREATENING RISKS FROM USE OF XTAMPZA ER

Addiction, Abuse, and Misuse

Because the use of XTAMPZA ER exposes patients and other users to the risks of opioid addiction, abuse, and misuse, which can lead to overdose and death, assess each patient's risk prior to prescribing and reassess all patients regularly for the development of these behaviors and conditions [see Warnings and Precautions (5.1)].

Life-Threatening Respiratory Depression

Serious, life-threatening, or fatal respiratory depression may occur with use of XTAMPZA ER, especially during initiation or following a dosage increase. To reduce the risk of respiratory depression, proper dosing and titration of XTAMPZA ER are essential [see Warnings and Precautions (5.2)].

Accidental Ingestion

Accidental ingestion of even one dose of XTAMPZA ER, especially by children, can result in a fatal overdose of oxycodone [see Warnings and Precautions (5.2)].

Risks From Concomitant Use With Benzodiazepines Or Other CNS Depressants

Concomitant use of opioids with benzodiazepines or other central nervous system (CNS) depressants, including alcohol, may result in profound sedation, respiratory depression, coma, and death. Reserve concomitant prescribing of XTAMPZA ER and benzodiazepines or other CNS depressants for use in patients for whom alternative treatment options are inadequate. [see Warnings and Precautions (5.3), Drug Interactions (7)].

Neonatal Opioid Withdrawal Syndrome (NOWS)

Advise pregnant women using opioids for an extended period of time of the risk of Neonatal Opioid Withdrawal Syndrome, which may be life-threatening if not recognized and treated. Ensure that management by neonatology experts will be available at delivery [see Warnings and Precautions (5.4)].

Opioid Analgesic Risk Evaluation and Mitigation Strategy (REMS)

Healthcare providers are strongly encouraged to complete a REMS-compliant education program and to counsel patients and caregivers on serious risks, safe use, and the importance of reading the Medication Guide with each prescription [see Warnings and Precautions (5.5)].

Cytochrome P450 3A4 Interaction

The concomitant use of XTAMPZA ER with all cytochrome P450 3A4 inhibitors may result in an increase in oxycodone plasma concentrations, which could increase or prolong adverse drug effects and may cause potentially fatal respiratory depression. In addition, discontinuation of a concomitantly used cytochrome P450 3A4 inducer may result in an increase in oxycodone plasma concentration. Regularly evaluate patients receiving XTAMPZA ER and any CYP3A4 inhibitor or inducer [see Warnings and Precautions (5.6), Drug Interactions (7),Clinical Pharmacology (12.3)].

1 INDICATIONS AND USAGE

XTAMPZA ER is indicated for the management of severe and persistent pain that requires an opioid analgesic and that cannot be adequately treated with alternative options, including immediate-release opioids.

Limitations of Use

- Because of the risks of addiction, abuse, misuse, overdose, and death, which can occur at any dosage or duration and persist over the course of therapy [see Warnings and Precautions (5.1)], reserve opioid analgesics, including XTAMPZA ER, for use in patients for whom alternative treatment options are ineffective, not tolerated, or would be otherwise inadequate to provide sufficient management of pain.
- XTAMPZA ER is not indicated as an as-needed (prn) analgesic.

2 DOSAGE AND ADMINISTRATION

2.1 Important Dosage and Administration Instructions

- XTAMPZA ER should be prescribed only by healthcare professionals who are knowledgeable about the use of extended-release/long-acting opioids and how to mitigate the associated risks.
- XTAMPZA ER single doses greater than 36 mg (equivalent to 40 mg oxycodone hydrochloride [HCl]) or a total daily dose greater than 72 mg (equivalent to 80 mg oxycodone HCl) are to be administered only to patients in whom tolerance to an opioid of comparable potency has been established. Patients who are opioid-tolerant are those receiving, for one week or longer, at least 60 mg oral morphine per day, 25 mcg transdermal fentanyl per hour, 30 mg oral oxycodone HCl per day, 8 mg oral hydromorphone per day, 25 mg oral oxymorphone per day, 60 mg oral hydrocodone per day, or an equianalgesic dose of another opioid.
- Use the lowest effective dosage for the shortest duration of time consistent with individual patient treatment goals [see Warnings and Precautions (5)]. Because the risk of overdose increases as opioid doses increase, reserve titration to higher doses of XTAMPZA ER for patients in whom lower doses are insufficiently effective and in whom the expected benefits of using a higher dose opioid clearly outweigh the substantial risks.
- Initiate the dosing regimen for each patient individually, taking into account the patient's underlying cause and severity of pain, prior analgesic treatment and response, and risk factors for addiction, abuse, and misuse [see Warnings and Precautions (5.1)].
- Respiratory depression can occur at any time during opioid therapy, especially when initiating and following dosage increases with XTAMPZA ER. Consider this risk when selecting an initial dose and when making dose adjustments [see Warnings and Precautions (5.2)].
- XTAMPZA ER is administered, twice daily, every 12 hours, and must be taken with food. Instruct patients to take XTAMPZA ER capsules with approximately the same amount of food for every dose in order to ensure consistent plasma levels are achieved [see Clinical Pharmacology (12.3)].
- Patients who are unable to swallow XTAMPZA ER should be instructed to sprinkle the capsule contents on soft foods or into a cup and then administer directly into the mouth and immediately swallow. XTAMPZA ER may also be administered through a gastrostomy or nasogastric feeding tube [see Dosage and Administration (2.7)].
- The maximum daily dose of XTAMPZA ER is 288 mg per day (eight 36 mg capsules, equivalent to 320 mg oxycodone HCl per day) as the safety of the excipients in XTAMPZA ER for doses over 288 mg/day has not been established.

2.2 Patient Access to an Opioid Overdose Reversal Agent for the Emergency Treatment of Opioid Overdose

Inform patients and caregivers about opioid overdose reversal agents (e.g., naloxone, nalmefene). Discuss the importance of having access to an opioid overdose reversal agent, especially if the patient has risk factors for overdose (e.g., concomitant use of CNS depressants, a history of opioid use disorder, or prior opioid overdose) or if there are household members (including children) or other close contacts at risk for accidental ingestion or opioid overdose. The presence of risk factors for overdose should not prevent the management of pain in any patient [see Warnings and Precautions (5.1, 5.2, 5.3)].

Discuss the options for obtaining an opioid overdose reversal agent (e.g., prescription, over-the-counter, or as part of a community-based program) [see Warnings and Precautions (5.2)].

There are important differences among the opioid overdose reversal agents, such as route of administration, product strength, approved patient age range, and pharmacokinetics. Be familiar with these differences, as outlined in the approved labeling for those products, prior to recommending or prescribing such an agent.

2.3 Initial Dosage

It is safer to underestimate a patient's 24-hour oral oxycodone dosage and provide rescue medication (e.g., immediate-release opioid) than to overestimate the 24-hour oral oxycodone dosage and manage adverse reactions due to an overdose. While useful tables of opioid equivalents are readily available, there is substantial inter-patient variability in the relative potency of different opioid drugs and products. Frequently reevaluate patients for signs and symptoms of opioid withdrawal and for signs of oversedation/toxicity after converting patients to XTAMPZA ER.

Use of XTAMPZA ER in Patients who are not Opioid Tolerant

The starting dose for patients who are not opioid tolerant is XTAMPZA ER 9 mg orally every 12 hours with food. Use of higher starting doses in patients who are not opioid tolerant may cause fatal respiratory depression [see Warnings and Precautions (5.2)].

Conversion from other Oral Oxycodone Formulations to XTAMPZA ER

XTAMPZA ER is formulated with oxycodone base. The following table describes the equivalent amount of oxycodone HCl present in other oxycodone products.

Table 1. Equivalence table for dosage strengths of oxycodone hydrochloride salt and oxycodone base (XTAMPZA ER)
Oxycodone Hydrochloride | Oxycodone base (XTAMPZA ER)
10 mg | 9 mg
15 mg | 13.5 mg
20 mg | 18 mg
30 mg | 27 mg
40 mg | 36 mg

Patients receiving other oral oxycodone formulations may be converted to XTAMPZA ER, using the same total daily dose of oxycodone, by administering one-half of the patient's total daily oral oxycodone dose as XTAMPZA ER every 12 hours with food. Because XTAMPZA ER is not bioequivalent to other oxycodone extended-release products (refer to Table 1), monitor patients for possible dosage adjustment.

Conversion from Methadone to XTAMPZA ER

Frequent evaluation is of particular importance when converting from methadone to other opioid agonists. The ratio between methadone and other opioid agonists may vary widely as a function of previous dose exposure. Methadone has a long half-life and can accumulate in the plasma.

Conversion from Fentanyl Transdermal System to XTAMPZA ER

Eighteen hours following the removal of the fentanyl transdermal system, XTAMPZA ER treatment can be initiated. Although there has been no systematic assessment of such conversion, a conservative oxycodone dose, approximately 9 mg (equivalent to 10 mg oxycodone HCl) every 12 hours of XTAMPZA ER, should be initially substituted for each 25 mcg/hr fentanyl transdermal system. Follow the patient closely during conversion from fentanyl transdermal system to XTAMPZA ER, as there is limited documented experience with this conversion.

Conversion from Other Opioid Analgesics to XTAMPZA ER

When XTAMPZA ER therapy is initiated, discontinue all other opioid analgesics other than those used on an as needed basis for breakthrough pain when appropriate.

There are no established conversion ratios for conversion from other opioids to XTAMPZA ER defined by clinical trials. Initiate dosing using XTAMPZA ER 9 mg orally every 12 hours with food.

2.4 Dosage Modifications in Patients with Hepatic Impairment

For patients with hepatic impairment, start dosing patients at 1/3 to 1/2 the usual starting dose followed by careful dose titration. Regularly evaluate for adverse events such as respiratory depression. Use of alternate analgesics is recommended for patients who require an XTAMPZA ER dose of less than 9 mg [see Use in Specific Populations (8.5), Clinical Pharmacology (12.3)].

2.5 Titration and Maintenance of Therapy

Individually titrate XTAMPZA ER to a dose that provides adequate analgesia and minimizes adverse reactions. Continually reevaluate patients receiving XTAMPZA ER to assess the maintenance of pain control and the relative incidence of adverse reactions, as well as to reassess for the development of addiction, abuse, and misuse. Frequent communication is important among the prescriber, other members of the healthcare team, the patient, and the caregiver/family during periods of changing analgesic requirements, including initial titration. During use of opioid therapy for an extended period of time, periodically reassess the continued need for the use of opioid analgesics.

Patients who experience breakthrough pain may require a dose increase of XTAMPZA ER or may need rescue medication with an appropriate dose of an immediate-release analgesic. If the level of pain increases after dose stabilization, attempt to identify the source of increased pain before increasing the XTAMPZA ER dose. If after increasing the dosage, unacceptable opioid-related adverse reactions are observed (including an increase in pain after a dosage increase), consider reducing the dosage [see Warnings and Precautions (5)]. Adjust the dosage to obtain an appropriate balance between management of pain and opioid-related adverse reactions.

Because steady-state plasma concentrations are approximated in 1 to 2 days, XTAMPZA ER dosage may be adjusted every 1 to 2 days. If unacceptable opioid-related adverse reactions are observed, the subsequent dose may be reduced. Adjust the dose to obtain an appropriate balance between management of pain and opioid-related adverse reactions.

There are no well-controlled clinical studies evaluating the safety and efficacy with dosing more frequently than every 12 hours. As a guideline, the total daily oxycodone dose usually can be increased by 25% to 50% of the current dose, each time an increase is clinically indicated.

2.6 Safe Reduction or Discontinuation of XTAMPZA ER

Do not rapidly reduce or abruptly discontinue XTAMPZA ER in patients who may be physically dependent on opioids. Rapid reduction or abrupt discontinuation of opioid analgesics in patients who are physically dependent on opioids has resulted in serious withdrawal symptoms, uncontrolled pain, and suicide. Rapid reduction or abrupt discontinuation has also been associated with attempts to find other sources of opioid analgesics, which may be confused with drug-seeking for abuse. Patients may also attempt to treat their pain or withdrawal symptoms with illicit opioids, such as heroin, and other substances.

When a decision has been made to decrease the dose or discontinue therapy in an opioid-dependent patient taking XTAMPZA ER, there are a variety of factors that should be considered, including the total daily dose of opioid (including XTAMPZA ER) the patient has been taking, the duration of treatment, the type of pain being treated, and the physical and psychological attributes of the patient. It is important to ensure ongoing care of the patient and to agree on an appropriate tapering schedule and follow-up plan so that patient and provider goals and expectations are clear and realistic. When opioid analgesics are being discontinued due to a suspected substance use disorder, evaluate and treat the patient, or refer for evaluation and treatment of the substance use disorder. Treatment should include evidence-based approaches, such as medication assisted treatment of opioid use disorder. Complex patients with co-morbid pain and substance use disorders may benefit from referral to a specialist.

There are no standard opioid tapering schedules that are suitable for all patients. Good clinical practice dictates a patient-specific plan to taper the dose of the opioid gradually. For patients on XTAMPZA ER who are physically opioid-dependent, initiate the taper by a small enough increment (e.g., no greater than 10% to 25% of the total daily dose) to avoid withdrawal symptoms, and proceed with dose-lowering at an interval of every 2 to 4 weeks. Patients who have been taking opioids for briefer periods of time may tolerate a more rapid taper.

It may be necessary to provide the patient with lower dosage strengths to accomplish a successful taper. Reassess the patient frequently to manage pain and withdrawal symptoms, should they emerge. Common withdrawal symptoms include restlessness, lacrimation, rhinorrhea, yawning, perspiration, chills, myalgia, and mydriasis. Other signs and symptoms also may develop, including irritability, anxiety, backache, joint pain, weakness, abdominal cramps, insomnia, nausea, anorexia, vomiting, diarrhea, or increased blood pressure, respiratory rate, or heart rate. If withdrawal symptoms arise, it may be necessary to pause the taper for a period of time or raise the dose of the opioid analgesic to the previous dose, and then proceed with a slower taper. In addition, evaluate patients for any changes in mood, emergence of suicidal thoughts, or use of other substances.

When managing patients taking opioid analgesics, particularly those who have been treated for an extended period of time, and/or with high doses for chronic pain, ensure that a multimodal approach to pain management, including mental health support (if needed), is in place prior to initiating an opioid analgesic taper. A multimodal approach to pain management may optimize the treatment of chronic pain, as well as assist with the successful tapering of the opioid analgesic [see Warnings and Precautions (5.14), Drug Abuse and Dependence (9.3)].

2.7 Administration of XTAMPZA ER

Instruct patients to always take XTAMPZA ER capsules with food and with approximately the same amount of food in order to ensure consistent plasma levels are achieved [see Dosage and Administration (2.1), Clinical Pharmacology (12.3)].

For patients who have difficulty swallowing, XTAMPZA ER can also be taken by sprinkling the capsule contents on soft foods or sprinkling the contents into a cup and then administering directly into the mouth or through a gastrostomy or nasogastric feeding tube. Patients who are unable to swallow a capsule should be instructed to:

1. Open the capsule.
2. Sprinkle the capsule contents (microspheres) onto a small amount of soft food (e.g., applesauce, pudding, yogurt, ice cream, or jam) or into a cup and then administer directly into the mouth and swallow immediately.
3. Rinse the mouth to ensure all capsule contents (microspheres) have been swallowed.
4. Discard the XTAMPZA ER capsule shells after the contents have been sprinkled on soft food or into a cup and then administered directly into the mouth.

The contents of the XTAMPZA ER capsules (microspheres) may be administered through a nasogastric tube or gastrostomy tube. When administering XTAMPZA ER through a nasogastric or gastrostomy tube:

1. Flush the tube with water.
2. Open an XTAMPZA ER capsule and carefully pour the microspheres directly into the tube. Do not pre-mix the capsule contents with the liquid that you will be using to flush them through the tube.
3. Draw up 15 mL of water into a syringe, insert the syringe into the tube, and flush the microspheres through the tube.
4. Repeat the flushing two more times, each with 10 mL of water, to ensure no microspheres remain in the tube.

Alternatively, milk or liquid nutritional supplement may be used as vehicles for flush and administration through feeding tubes.

3 DOSAGE FORMS AND STRENGTHS

XTAMPZA ER capsules contain yellow to light brown microspheres, and each available strength has an outer opaque capsule with colors as identified below.

Strength | Capsule Description
9 mg (equivalent to 10 mg oxycodone HCl) | Size 3, ivory cap printed with "XTAMPZA ER" and white body printed with "9 mg"
13.5 mg (equivalent to 15 mg oxycodone HCl) | Size 2, Swedish orange cap printed with "XTAMPZA ER" and white body printed with "13.5 mg"
18 mg (equivalent to 20 mg oxycodone HCl) | Size 1, rich yellow cap printed with "XTAMPZA ER" and white body printed with "18 mg"
27 mg (equivalent to 30 mg oxycodone HCl) | Size 0, light gray cap printed with "XTAMPZA ER" and white body printed with "27 mg"
36 mg (equivalent to 40 mg oxycodone HCl) | Size 00, flesh color cap printed with "XTAMPZA ER" and white body printed with "36 mg"

4 CONTRAINDICATIONS

XTAMPZA ER is contraindicated in patients with:

- Significant respiratory depression [see Warnings and Precautions (5.2)]
- Acute or severe bronchial asthma in an unmonitored setting or in the absence of resuscitative equipment [see Warnings and Precautions (5.8)]
- Known or suspected gastrointestinal obstruction, including paralytic ileus [see Warnings and Precautions (5.12)]
- Hypersensitivity (e.g., anaphylaxis) to oxycodone.

5 WARNINGS AND PRECAUTIONS

5.1 Addiction, Abuse, and Misuse

XTAMPZA ER contains oxycodone, a Schedule II controlled substance. As an opioid, XTAMPZA ER exposes users to the risks of addiction, abuse, and misuse [see Drug Abuse and Dependence (9)].

Although the risk of addiction in any individual is unknown, it can occur in patients appropriately prescribed XTAMPZA ER. Addiction can occur at recommended dosages and if the drug is misused or abused. The risk of opioid-related overdose or overdose-related death is increased with higher opioid doses, and this risk persists over the course of therapy. In postmarketing studies, addiction, abuse, misuse, and fatal and non-fatal opioid overdose were observed in patients with long-term opioid use [see Adverse Reactions (6.2)].

Assess each patient's risk for opioid addiction, abuse, or misuse prior to prescribing XTAMPZA ER, and reassess all patients receiving XTAMPZA ER for the development of these behaviors or conditions. Risks are increased in patients with a personal or family history of substance abuse (including drug or alcohol abuse or addiction) or mental illness (e.g., major depression). The potential for these risks should not, however, prevent the proper management of pain in any given patient. Patients at increased risk may be prescribed opioids such as XTAMPZA ER but use in such patients necessitates intensive counseling about the risks and proper use of XTAMPZA ER along with frequent evaluation for signs of addiction, abuse, and misuse. Consider recommending or prescribing an opioid overdose reversal agent [see Dosage and Administration (2.2), Warnings and Precautions (5.2)].

Abuse or misuse of XTAMPZA ER by snorting or by injecting the dissolved product can result in overdose and death [see Overdosage (10)].

Opioids are sought for nonmedical use and are subject to diversion from legitimate prescribed use. Consider these risks when prescribing or dispensing XTAMPZA ER. Strategies to reduce these risks include prescribing the drug in the smallest appropriate quantity and advising the patient on careful storage of the drug during the course of treatment and the proper disposal of unused drug. Contact local state professional licensing board or state-controlled substances authority for information on how to prevent and detect abuse or diversion of this product.

5.2 Life-Threatening Respiratory Depression

Serious, life-threatening, or fatal respiratory depression has been reported with the use of opioids, even when used as recommended. Respiratory depression, if not immediately recognized and treated, may lead to respiratory arrest and death. Management of respiratory depression may include close observation, supportive measures, and use of opioid overdose reversal agents, depending on the patient's clinical status [see Overdosage (10)]. Carbon dioxide (CO2) retention from opioid-induced respiratory depression can exacerbate the sedating effects of opioids.

While serious, life-threatening, or fatal respiratory depression can occur at any time during the use of XTAMPZA ER, the risk is greatest during the initiation of therapy or following a dosage increase.

To reduce the risk of respiratory depression, proper dosing and titration of XTAMPZA ER are essential [see Dosage and Administration (2)]. Overestimating the XTAMPZA ER dose when converting patients from another opioid product can result in a fatal overdose with the first dose.

Accidental ingestion of even one dose of XTAMPZA ER, especially by children, can result in respiratory depression and death due to an overdose of oxycodone.

Educate patients and caregivers on how to recognize respiratory depression and emphasize the importance of calling 911 or getting emergency medical help right away in the event of a known or suspected overdose.

Opioids can cause sleep-related breathing disorders including central sleep apnea (CSA) and sleep-related hypoxemia. Opioid use increases the risk of CSA in a dose-dependent fashion. In patients who present with CSA, consider decreasing the opioid dosage using best practices for opioid taper [see Dosage and Administration (2.6)].

Patient Access to an Opioid Overdose Reversal Agent for the Emergency Treatment of Opioid Overdose

Inform patients and caregivers about opioid overdose reversal agents (e.g., naloxone, nalmefene). Discuss the importance of having access to an opioid overdose reversal agent, especially if the patient has risk factors for overdose (e.g., concomitant use of CNS depressants, a history of opioid use disorder, or prior opioid overdose) or if there are household members (including children) or other close contacts at risk for accidental ingestion or opioid overdose. The presence of risk factors for overdose should not prevent the management of pain in any patient [see Warnings and Precautions (5.1, 5.2)].

Discuss the options for obtaining an opioid overdose reversal agent (e.g., prescription, over-the-counter, or as part of a community-based program).

There are important differences among the opioid overdose reversal agents, such as route of administration, product strength, approved patient age range, and pharmacokinetics. Be familiar with these differences, as outlined in the approved labeling for those products, prior to recommending or prescribing such an agent. outlined in the approved labeling for those products, prior to recommending or prescribing such an agent.

Educate patients and caregivers on how to recognize respiratory depression, and how to use an opioid overdose reversal agent for the emergency treatment of opioid overdose. Emphasize the importance of calling 911 or getting emergency medical help, even if an opioid overdose reversal agent is administered [see Dosage and Administration (2.2), Warnings and Precautions (5.1, 5.3), Overdosage (10)].

5.3 Risks from Concomitant Use with Benzodiazepines or Other CNS Depressants

Profound sedation, respiratory depression, coma, and death may result from the concomitant use of XTAMPZA ER with benzodiazepines and/or other CNS depressants, including alcohol (e.g., non-benzodiazepine sedatives/hypnotics, anxiolytics, tranquilizers, muscle relaxants, general anesthetics, antipsychotics, gabapentinoids [gabapentin or pregabalin], and other opioids). Because of these risks, reserve concomitant prescribing of these drugs for use in patients for whom alternative treatment options are inadequate.

Observational studies have demonstrated that concomitant use of opioid analgesics and benzodiazepines increases the risk of drug-related mortality compared to use of opioid analgesics alone. Because of similar pharmacological properties, it is reasonable to expect similar risk with the concomitant use of other CNS depressant drugs with opioid analgesics [see Drug Interactions (7)].

If the decision is made to prescribe a benzodiazepine or other CNS depressant concomitantly with an opioid analgesic, prescribe the lowest effective dosages and minimum durations of concomitant use. In patients already receiving an opioid analgesic, prescribe a lower initial dose of the benzodiazepine or other CNS depressants than indicated in the absence of an opioid, and titrate based on clinical response. If an opioid analgesic is initiated in a patient already taking a benzodiazepine or other CNS depressant, prescribe a lower initial dose of the opioid analgesic, and titrate based on clinical response. Inform patients and caregivers of this potential interaction and educate them on the signs and symptoms of respiratory depression (including sedation).

If concomitant use is warranted, consider recommending or prescribing an opioid overdose reversal agent for the emergency treatment of opioid overdose [see Dosage and Administration (2.2), Warnings and Precautions (5.2), Overdosage (10)].

Advise both patients and caregivers about the risks of respiratory depression and sedation when XTAMPZA ER is used with benzodiazepines or other CNS depressants (including alcohol and illicit drugs). Advise patients not to drive or operate heavy machinery until the effects of concomitant use of the benzodiazepine or other CNS depressant have been determined. Screen patients for risk of substance use disorders, including opioid abuse and misuse, and warn them of the risk for overdose and death associated with the use of additional CNS depressants including alcohol and illicit drugs [see Drug Interactions (7)].

5.4 Neonatal Opioid Withdrawal Syndrome

Use of XTAMPZA ER for an extended period of time during pregnancy can result in withdrawal in the neonate. Neonatal opioid withdrawal syndrome, unlike opioid withdrawal syndrome in adults, may be life-threatening if not recognized and treated, and requires management according to protocols developed by neonatology experts. Observe newborns for signs of neonatal opioid withdrawal syndrome and manage accordingly. Advise pregnant women using opioids for an extended period of time of the risk of neonatal opioid withdrawal syndrome and ensure that appropriate treatment will be available [see Use in Specific Populations (8.1)].

5.5 Opioid Analgesic Risk Evaluation and Mitigation Strategy (REMS)

To ensure that the benefits of opioid analgesics outweigh the risks of addiction, abuse, and misuse, the Food and Drug Administration (FDA) has required a Risk Evaluation and Mitigation Strategy (REMS) for these products. Under the requirements of the REMS, drug companies with approved opioid analgesic products must make REMS-compliant education programs available to healthcare providers. Healthcare providers are strongly encouraged to do all of the following:

- Complete a REMS-compliant education program offered by an accredited provider of continuing education (CE) or another education program that includes all the elements of the FDA Education Blueprint for Health Care Providers Involved in the Management or Support of Patients with Pain.
- Discuss the safe use, serious risks, and proper storage and disposal of opioid analgesics with patients and/or their caregivers every time these medicines are prescribed. The Patient Counseling Guide (PCG) can be obtained at this link: www.fda.gov/OpioidAnalgesicREMSPCG.
- Emphasize to patients and their caregivers the importance of reading the Medication Guide that they will receive from their pharmacist every time an opioid analgesic is dispensed to them.
- Consider using other tools to improve patient, household, and community safety, such as patient-prescriber agreements that reinforce patient-prescriber responsibilities.

To obtain further information on the opioid analgesic REMS and for a list of accredited REMS CME/CE, call 1-800-503-0784, or log on to www.opioidanalgesicrems.com. The FDA Blueprint can be found at www.fda.gov/OpioidAnalgesicREMSBlueprint.

5.6 Risks of Concomitant Use or Discontinuation of Cytochrome P450 3A4 Inhibitors and Inducers

Concomitant use of XTAMPZA ER with a CYP3A4 inhibitor, such as macrolide antibiotics (e.g., erythromycin), azole-antifungal agents (e.g., ketoconazole), and protease inhibitors (e.g., ritonavir), may increase plasma concentrations of oxycodone and prolong opioid adverse reactions, which may cause potentially fatal respiratory depression [see Warnings and Precautions (5.2)], particularly when an inhibitor is added after a stable dose of XTAMPZA ER is achieved. Similarly, discontinuation of a CYP3A4 inducer, such as rifampin, carbamazepine, and phenytoin, in XTAMPZA ER-treated patients may increase oxycodone plasma concentrations and prolong opioid adverse reactions. When using XTAMPZA ER with CYP3A4 inhibitors or discontinuing CYP3A4 inducers in XTAMPZA ER-treated patients, evaluate patients at frequent intervals and consider dosage reduction of XTAMPZA ER until stable drug effects are achieved [see Drug Interactions (7)].

Concomitant use of XTAMPZA ER with CYP3A4 inducers or discontinuation of a CYP3A4 inhibitor could decrease oxycodone plasma concentrations, decrease opioid efficacy or, possibly, lead to a withdrawal syndrome in a patient who had developed physical dependence to oxycodone. When using XTAMPZA ER with CYP3A4 inducers or discontinuing CYP3A4 inhibitors, evaluate patients at frequent intervals and consider increasing the opioid dosage if needed to maintain adequate analgesia or if symptoms of opioid withdrawal occur [see Drug Interactions (7)].

5.7 Opioid-Induced Hyperalgesia and Allodynia

Opioid-Induced Hyperalgesia (OIH) occurs when an opioid analgesic paradoxically causes an increase in pain, or an increase in sensitivity to pain. This condition differs from tolerance, which is the need for increasing doses of opioids to maintain a defined effect [see Dependence (9.3)]. Symptoms of OIH include (but may not be limited to) increased levels of pain upon opioid dosage increase, decreased levels of pain upon opioid dosage decrease, or pain from ordinarily non-painful stimuli (allodynia). These symptoms may suggest OIH only if there is no evidence of underlying disease progression, opioid tolerance, opioid withdrawal, or addictive behavior.

Cases of OIH have been reported, both with short-term and longer-term use of opioid analgesics. Though the mechanism of OIH is not fully understood, multiple biochemical pathways have been implicated. Medical literature suggests a strong biologic plausibility between opioid analgesics and OIH and allodynia. If a patient is suspected to be experiencing OIH, carefully consider appropriately decreasing the dose of the current opioid analgesic or opioid rotation (safely switching the patient to a different opioid moiety) [see Dosage and Administration (2.6), Warnings and Precautions (5.14)].

5.8 Risk of Life-Threatening Respiratory Depression in Patients with Chronic Pulmonary Disease or in Elderly, Cachectic, or Debilitated Patients

The use of XTAMPZA ER in patients with acute or severe bronchial asthma in an unmonitored setting or in the absence of resuscitative equipment is contraindicated.

Patients with Chronic Pulmonary Disease: XTAMPZA ER-treated patients with significant chronic obstructive pulmonary disease or cor pulmonale, and those with a substantially decreased respiratory reserve, hypoxia, hypercapnia, or pre-existing respiratory depression are at increased risk of decreased respiratory drive including apnea, even at recommended dosages of XTAMPZA ER [see Warnings and Precautions (5.2)].

Elderly, Cachectic, or Debilitated Patients: Life-threatening respiratory depression is more likely to occur in elderly, cachectic, or debilitated patients as they may have altered pharmacokinetics or altered clearance compared to younger, healthier patients.

Regularly evaluate patients, particularly when initiating and titrating XTAMPZA ER and when XTAMPZA ER is given concomitantly with other drugs that depress respiration [see Warnings and Precautions (5.2, 5.3)]. Alternatively, consider the use of non-opioid analgesics in these patients. Use an alternative analgesic for patients who require a dose of XTAMPZA ER less than 9 mg.

5.9 Adrenal Insufficiency

Cases of adrenal insufficiency have been reported with opioid use, more often following greater than one month of use. Presentation of adrenal insufficiency may include non-specific symptoms and signs including nausea, vomiting, anorexia, fatigue, weakness, dizziness, and low blood pressure. If adrenal insufficiency is suspected, confirm the diagnosis with diagnostic testing as soon as possible. If adrenal insufficiency is diagnosed, treat with physiologic replacement doses of corticosteroids. Wean the patient off of the opioid to allow adrenal function to recover and continue corticosteroid treatment until adrenal function recovers. Other opioids may be tried as some cases reported use of a different opioid without recurrence of adrenal insufficiency. The information available does not identify any particular opioids as being more likely to be associated with adrenal insufficiency.

5.10 Severe Hypotension

XTAMPZA ER may cause severe hypotension including orthostatic hypotension and syncope in ambulatory patients. There is an increased risk in patients whose ability to maintain blood pressure has already been compromised by a reduced blood volume or concurrent administration of certain CNS depressant drugs (e.g., phenothiazines or general anesthetics) [see Drug Interactions (7)]. Regularly evaluate these patients for signs of hypotension after initiating or titrating the dosage of XTAMPZA ER. In patients with circulatory shock, XTAMPZA ER may cause vasodilation that can further reduce cardiac output and blood pressure. Avoid the use of XTAMPZA ER in patients with circulatory shock.

5.11 Risks of Use in Patients with Increased Intracranial Pressure, Brain Tumors, Head Injury, or Impaired Consciousness

In patients who may be susceptible to the intracranial effects of CO2 retention (e.g., those with evidence of increased intracranial pressure or brain tumors), XTAMPZA ER may reduce respiratory drive, and the resultant CO2 retention can further increase intracranial pressure. Monitor such patients for signs of sedation and respiratory depression, particularly when initiating therapy with XTAMPZA ER.

Opioids may also obscure the clinical course in a patient with a head injury. Avoid the use of XTAMPZA ER in patients with impaired consciousness or coma.

5.12 Risks of Gastrointestinal Complications

XTAMPZA ER is contraindicated in patients with gastrointestinal obstruction, including paralytic ileus.

The oxycodone in XTAMPZA ER may cause spasm of the sphincter of Oddi. Opioids may cause increases in the serum amylase. Regularly evaluate with biliary tract disease, including acute pancreatitis, for worsening symptoms.

Cases of opioid-induced esophageal dysfunction (OIED) have been reported in patients taking opioids. The risk of OIED may increase as the dose and/or duration of opioids increases. Regularly evaluate patients for signs and symptoms of OIED (e.g., dysphagia, regurgitation, non-cardiac chest pain) and, if necessary, adjust opioid therapy as clinically appropriate [see Clinical Pharmacology (12.2)]. .

5.13 Increased Risk of Seizures in Patients with Seizure Disorders

The oxycodone in XTAMPZA ER may increase the frequency of seizures in patients with seizure disorders and may increase the risk of seizures in other clinical settings associated with seizures. Regularly evaluate patients with a history of seizure disorders for worsened seizure control during XTAMPZA ER therapy.

5.14 Withdrawal

Do not rapidly reduce or abruptly discontinue XTAMPZA ER in a patient physically dependent on opioids. When discontinuing XTAMPZA ER in a physically dependent patient, gradually taper the dosage. Rapid tapering of oxycodone in a patient physically dependent on opioids may lead to a withdrawal syndrome and return of pain [see Dosage and Administration (2.6), Drug Abuse and Dependence (9.3)].

Additionally, avoid the use of mixed agonist/antagonist (e.g., pentazocine, nalbuphine, and butorphanol) or partial agonist (e.g., buprenorphine) analgesics in patients who have received or are receiving a course of therapy with a full opioid agonist analgesic, including XTAMPZA ER. In these patients, mixed agonist/antagonist and partial agonist analgesics may reduce the analgesic effect and/or may precipitate withdrawal symptoms [see Dosage and Administration (2.6), Drug Interactions (7)].

5.15 Risks of Driving and Operating Machinery

XTAMPZA ER may impair the mental or physical abilities needed to perform potentially hazardous activities such as driving a car or operating machinery. Warn patients not to drive or operate dangerous machinery unless they are tolerant to the effects of XTAMPZA ER and know how they will react to the medication.

5.16 Laboratory Monitoring

Not every urine drug test for "opioids" or "opiates" detects oxycodone reliably, especially those designed for in-office use. Further, many laboratories will report urine drug concentrations below a specified "cut-off" value as "negative". Therefore, if urine testing for oxycodone is considered in the clinical management of an individual patient, ensure that the sensitivity and specificity of the assay is appropriate, and consider the limitations of the testing used when interpreting results.

6 ADVERSE REACTIONS

The following serious adverse reactions are described elsewhere in the labeling:

- Addiction, Abuse, and Misuse [see Warnings and Precautions (5.1)]
- Life-Threatening Respiratory Depression [see Warnings and Precautions (5.2)]
- Interactions with Benzodiazepines or Other CNS Depressants [see Warnings and Precautions (5.3)]
- Neonatal Opioid Withdrawal Syndrome [see Warnings and Precautions (5.4)]
- Opioid-Induced Hyperalgesia and Allodynia [see Warnings and Precautions (5.7)]
- Adrenal Insufficiency [see Warnings and Precautions (5.9)]
- Severe Hypotension [see Warnings and Precautions (5.10)]
- Gastrointestinal Adverse Reactions [see Warnings and Precautions (5.12)]
- Seizures [see Warnings and Precautions (5.13)]
- Withdrawal [see Warnings and Precautions (5.14)]

6.1 Clinical Trial Experience

Because clinical trials are conducted under widely varying conditions, adverse reaction rates observed in the clinical trials of a drug cannot be directly compared to rates in the clinical trials of another drug and may not reflect the rates observed in practice.

The safety of XTAMPZA ER was evaluated in a Phase 3, randomized-withdrawal, double-blind clinical trial involving 740 patients with moderate-to-severe chronic lower back pain. In the double-blind maintenance phase, 389 patients were randomized and 193 patients were assigned to the XTAMPZA ER treatment group.

The most common AEs (>5%) reported by patients in the Phase 3 clinical trial during the titration phase were: nausea (16.6%), headache (13.9%), constipation (13.0%), somnolence (8.8%), pruritus (7.4%), vomiting (6.4%), and dizziness (5.7%).

The most common adverse reactions (>5%) reported by patients in the Phase 3 clinical trial comparing XTAMPZA ER with placebo are shown in Table below:

Table 2: Common Adverse Reactions (>5%)
 | Titration | Maintenance
Adverse Reaction | XTAMPZA ER (n = 740) (%) | XTAMPZA ER (n = 193) (%) | Placebo (n = 196) (%)
Nausea | 16.6 | 10.9 | 4.6
Headache | 13.9 | 6.2 | 11.7
Constipation | 13.0 | 5.2 | 0.5
Somnolence | 8.8 | <1 | <1
Pruritus | 7.4 | 2.6 | 1.5
Vomiting | 6.4 | 4.1 | 1.5
Dizziness | 5.7 | 1.6 | 0

In the Phase 3 clinical trial, the following adverse reactions were reported in patients treated with XTAMPZA ER with incidences of 1% to 5%:

Eye disorders: vision blurred

Gastrointestinal disorders: abdominal pain, upper abdominal pain, diarrhea, gastroesophageal reflux disease

General disorders and administration site conditions: chills, drug withdrawal syndrome, fatigue, irritability, edema, pyrexia

Injury, poisoning and procedural complications: excoriation

Metabolism and nutrition disorders: decreased appetite, hyperglycemia

Musculoskeletal and connective tissue disorders: arthralgia, back pain, musculoskeletal pain, myalgia

Nervous system disorders: migraine, tremor

Psychiatric disorders: anxiety, insomnia, withdrawal syndrome

Respiratory, thoracic and mediastinal disorders: cough, oropharyngeal pain

Skin and subcutaneous tissue disorders: hyperhidrosis, rash

Vascular disorders: hot flush, hypertension

In the Phase 3 clinical trial, the following treatment-related adverse reactions were reported in patients treated with XTAMPZA ER with incidences of less than 1% of patients.

Investigations: increased gamma-glutamyl transferase, increased heart rate

Nervous system disorders: lethargy, memory impairment, poor-quality sleep

Psychiatric disorders: abnormal dreams, euphoric mood, restlessness

Respiratory, thoracic and mediastinal disorders: dyspnea

Skin and subcutaneous tissue disorders: night sweats

6.2 Postmarketing Experience

The following adverse reactions have been identified during post approval use of oxycodone. Because these reactions are reported voluntarily from a population of uncertain size, it is not always possible to reliably estimate their frequency or establish a causal relationship to drug exposure.

Serotonin syndrome: Cases of serotonin syndrome, a potentially life-threatening condition, have been reported during concomitant use of opioids with serotonergic drugs.

Adrenal insufficiency: Cases of adrenal insufficiency have been reported with opioid use, more often following greater than one month of use.

Anaphylaxis: Anaphylaxis has been reported with ingredients contained in XTAMPZA ER.

Androgen deficiency: Cases of androgen deficiency have occurred with use of opioids for an extended period of time [see Clinical Pharmacology (12.2)].

Hyperalgesia and Allodynia: Cases of hyperalgesia and allodynia have been reported with opioid therapy of any duration [see Warnings and Precautions (5.7)].

Hypoglycemia: Cases of hypoglycemia have been reported in patients taking opioids. Most reports were in patients with at least one predisposing risk factor (e.g., diabetes).

Opioid-induced esophageal dysfunction (OIED): Cases of OIED have been reported in patients taking opioids and may occur more frequently in patients taking higher doses of opioids, and/or in patients taking opioids longer term [see Warnings and Precautions (5.12)].

Adverse Reactions from Observational Studies

A prospective, observational cohort study estimated the risks of addiction, abuse, and misuse in patients initiating long-term use of Schedule II opioid analgesics between 2017 and 2021. Study participants included in one or more analyses had been enrolled in selected insurance plans or health systems for at least one year, were free of at least one outcome at baseline, completed a minimum number of follow-up assessments, and either: 1) filled multiple extended-release/long-acting opioid analgesic prescriptions during a 90- day period (n=978); or 2) filled any Schedule II opioid analgesic prescriptions covering at least 70 of 90 days (n=1,244). Those included also had no dispensing of the qualifying opioids in the previous 6 months.

Over 12 months:

- approximately 1% to 6% of participants across the two cohorts newly met criteria for addiction, as assessed with two validated interview-based measures of moderate-to-severe opioid use disorder based on Diagnostic and Statistical Manual of Mental Disorders, Fifth Edition (DSM-5) criteria, and
- approximately 9% and 22% of participants across the two cohorts newly met criteria for prescription opioid abuse and misuse [defined in Drug Abuse and Dependence (9.2)], respectively, as measured with a validated self-reported instrument.

A retrospective, observational cohort study estimated the risk of opioid-involved overdose or opioid overdose-related death in patients with new long-term use of Schedule II opioid analgesics from 2006 through 2016 (n=220,249). Included patients had been enrolled in either one of two commercial insurance programs, one managed care program, or one Medicaid program for at least 9 months. New long-term use was defined as having Schedule II opioid analgesic prescriptions covering at least 70 days' supply over the 3 months prior to study entry and none during the preceding 6 months. Patients were excluded if they had an opioid-involved overdose in the 9 months prior to study entry. Overdose was measured using a validated medical code-based algorithm with linkage to the National Death Index database. The 5-year cumulative incidence estimates for opioid-involved overdose or opioid overdose-related death ranged from approximately 1.5% to 4% across study sites, counting only the first event during follow-up. Approximately 17% of first opioid overdoses observed over the entire study period (5-11 years, depending on the study site) were fatal. Higher baseline opioid dose was the strongest and most consistent predictor of opioid-involved overdose or opioid overdose-related death. Study exclusion criteria may have selected patients at lower risk of overdose, and substantial loss to follow-up (approximately 80%) also may have biased estimates.

The risk estimates from the studies described above may not be generalizable to all patients receiving opioid analgesics, such as those with exposures shorter or longer than the duration evaluated in the studies.

7 DRUG INTERACTIONS

Table includes clinically significant drug interactions with XTAMPZA ER.

Table 3: Clinically Significant Drug Interactions with XTAMPZA ER
Inhibitors of CYP3A4 and CYP2D6
Clinical Impact: | The concomitant use of XTAMPZA ER and CYP3A4 inhibitors can increase the plasma concentration of oxycodone, resulting in increased or prolonged opioid effects. These effects could be more pronounced with concomitant use of XTAMPZA ER and CYP2D6 and CYP3A4 inhibitors, particularly when an inhibitor is added after a stable dose of XTAMPZA ER is achieved [see Warnings and Precautions (5.6)]. After stopping a CYP3A4 inhibitor, as the effects of the inhibitor decline, the oxycodone plasma concentration will decrease [see Clinical Pharmacology (12.3)], resulting in decreased opioid efficacy or a withdrawal syndrome in patients who had developed physical dependence to oxycodone.
Intervention: | If concomitant use is necessary, consider dosage reduction of XTAMPZA ER until stable drug effects are achieved. Evaluate patients at frequent intervals for respiratory depression and sedation. If a CYP3A4 inhibitor is discontinued, consider increasing the XTAMPZA ER dosage until stable drug effects are achieved. Assess for signs of opioid withdrawal.
Examples: | Macrolide antibiotics (e.g., erythromycin), azole-antifungal agents (e.g., ketoconazole), protease inhibitors (e.g., ritonavir)
CYP3A4 Inducers
Clinical Impact: | The concomitant use of XTAMPZA ER and CYP3A4 inducers can decrease the plasma concentration of oxycodone [see Clinical Pharmacology (12.3)], resulting in decreased efficacy or onset of a withdrawal syndrome in patients who have developed physical dependence to oxycodone [see Warnings and Precautions (5.6)]. After stopping a CYP3A4 inducer, as the effects of the inducer decline, the oxycodone plasma concentration will increase [see Clinical Pharmacology (12.3)], which could increase or prolong both the therapeutic effects and adverse reactions and may cause serious respiratory depression.
Intervention: | If concomitant use is necessary, consider increasing the XTAMPZA ER dosage until stable drug effects are achieved [see Dosage and Administration (2.5)]. Evaluate patients for signs of opioid withdrawal. If a CYP3A4 inducer is discontinued, consider XTAMPZA ER dosage reduction and evaluate patients at frequent intervals for signs of respiratory depression and sedation.
Examples: | Rifampin, carbamazepine, phenytoin
Benzodiazepines and other Central Nervous System (CNS) Depressants
Clinical Impact: | Due to additive pharmacological effect, the concomitant use of benzodiazepines or other CNS depressants including alcohol, increases the risk of respiratory depression, profound sedation, coma, and death [see Warnings and Precautions (5.3)].
Intervention: | Reserve concomitant prescribing of these drugs for use in patients for whom alternative treatment options are inadequate. Limit dosages and durations to the minimum required. Inform patients and caregivers of this potential interaction and educate them on the signs and symptoms of respiratory depression (including sedation). If concomitant use is warranted, consider recommending or prescribing an opioid overdose reversal agent [see Dosage and Administration (2.2), Warnings and Precautions (5.1, 5.2, 5.3)].
Examples | Benzodiazepines and other sedatives/hypnotics, anxiolytics, tranquilizers, muscle relaxants, general anesthetics, antipsychotics, gabapentinoids (gabapentin or pregabalin), other opioids, alcohol
Serotonergic Drugs
Clinical Impact: | The concomitant use of opioids with other drugs that affect the serotonergic neurotransmitter system has resulted in serotonin syndrome.
Intervention: | If concomitant use is warranted, frequently evaluate the patient, particularly during treatment initiation and dose adjustment. Discontinue XTAMPZA ER if serotonin syndrome is suspected.
Examples: | Selective serotonin reuptake inhibitors (SSRIs), serotonin and norepinephrine reuptake inhibitors (SNRIs), tricyclic antidepressants (TCAs), triptans, 5-HT3 receptor antagonists, drugs that effect the serotonin neurotransmitter system (e.g., mirtazapine, trazodone, tramadol), certain muscle relaxants (i.e., cyclobenzaprine, metaxalone), monoamine oxidase inhibitors (those intended to treat psychiatric disorders and also others, such as linezolid and intravenous methylene blue)
Monoamine Oxidase Inhibitors (MAOIs)
Clinical Impact: | MAOI interactions with opioids may manifest as serotonin syndrome or opioid toxicity (e.g., respiratory depression, coma) [see Warnings and Precautions (5.2)].
Intervention: | The use of XTAMPZA ER is not recommended for patients taking MAOIs or within 14 days of stopping such treatment.
Examples: | phenelzine, tranylcypromine, linezolid
Mixed Agonist/Antagonist and Partial Agonist Opioid Analgesics
Clinical Impact: | May reduce the analgesic effect of XTAMPZA ER and/or precipitate withdrawal symptoms.
Intervention: | Avoid concomitant use.
Examples: | Butorphanol, nalbuphine, pentazocine, buprenorphine
Muscle Relaxants
Clinical Impact: | Oxycodone may enhance the neuromuscular blocking action of skeletal muscle relaxants and produce an increased degree of respiratory depression.
Intervention: | Because respiratory depression may be greater than otherwise expected, decrease the dosage of XTAMPZA ER and/or the muscle relaxant as necessary. Due to the risk of respiratory depression with concomitant use of skeletal muscle relaxants and opioids, consider recommending or prescribing an opioid overdose reversal agent [see Dosage and Administration (2.2), Warnings and Precautions (5.2, 5.3)].
Examples: | Cyclobenzaprine, metaxalone
Diuretics
Clinical Impact: | Opioids can reduce the efficacy of diuretics by inducing the release of antidiuretic hormone.
Intervention: | Evaluate patients for signs of diminished diuresis and/or effects on blood pressure and increase the dosage of the diuretic as needed.
Anticholinergic Drugs
Clinical Impact: | The concomitant use of anticholinergic drugs may increase risk of urinary retention and/or severe constipation, which may lead to paralytic ileus.
Intervention: | Evaluate patients for signs of urinary retention or reduced gastric motility when XTAMPZA ER is used concomitantly with anticholinergic drugs.

8 USE IN SPECIFIC POPULATIONS

8.1 Pregnancy

Risk Summary

Use of opioid analgesics for an extended period of time during pregnancy may cause neonatal opioid withdrawal syndrome [see Warnings and Precautions (5.4)]. There are no available data with XTAMPZA ER in pregnant women to inform a drug-associated risk for major birth defects and miscarriage. In animal reproduction studies, there was no embryo-fetal toxicity when oxycodone hydrochloride was orally administered to rats and rabbits, during the period of organogenesis, at doses 1.3 to 40 times the adult human dose of 60 mg/day, respectively. In a pre- and postnatal toxicity study, when oxycodone was orally administered to rats, there was transiently decreased pup body weight during lactation and the early post-weaning period at the dose equivalent to an adult dose of 160 mg/day. In several published studies, treatment of pregnant rats with oxycodone hydrochloride at clinically relevant doses and below resulted in neurobehavioral effects in offspring [see Data]. Based on animal data, advise pregnant women of the potential risk to a fetus.

The background risk of major birth defects and miscarriage for the indicated population is unknown. All pregnancies have a background risk of birth defect, loss, or other adverse outcomes. In the U.S. general population, the estimated background risk of major birth defects and miscarriage in clinically recognized pregnancies is 2 to 4% and 15 to 20%, respectively.

Clinical Considerations

Fetal/neonatal adverse reactions

Use of opioid analgesics for an extended period of time during pregnancy for medical or nonmedical purposes can result in physical dependence in the neonate and neonatal opioid withdrawal syndrome shortly after birth.

Neonatal opioid withdrawal syndrome presents as irritability, hyperactivity and abnormal sleep pattern, high-pitched cry, tremor, vomiting, diarrhea and failure to gain weight. The onset, duration of use, and severity of neonatal opioid withdrawal syndrome may vary based on the specific opioid used, duration of use, timing and amount of last maternal use, and rate of elimination of the drug by the newborn. Observe newborns for symptoms of neonatal opioid withdrawal syndrome and manage accordingly [see Warnings and Precautions (5.4)].

Labor or delivery

Opioids cross the placenta and may produce respiratory depression and psycho-physiologic effects in neonates. An opioid overdose reversal agent, such as naloxone or nalmefene, must be available for reversal of opioid induced respiratory depression in the neonate. XTAMPZA ER is not recommended for use in pregnant women during or immediately prior to labor, when other analgesic techniques are more appropriate. Opioid analgesics, including XTAMPZA ER, can prolong labor through actions which temporarily reduce the strength, duration, and frequency of uterine contractions. However, this effect is not consistent and may be offset by an increased rate of cervical dilatation, which tends to shorten labor. Monitor neonates exposed to opioid analgesics during labor for signs of excess sedation and respiratory depression.

Data

Animal Data

Studies with oral doses of oxycodone hydrochloride in rats up to 8 mg/kg/day and rabbits up to 125 mg/kg/day, equivalent to 1.3 and 40 times an adult human dose of 160 mg/day, respectively on a mg/m^2 basis, did not reveal evidence of harm to the fetus due to oxycodone. In a pre- and postnatal toxicity study, female rats received oxycodone during gestation and lactation. There were no drug-related effects on reproductive performance in these females or any long-term developmental or reproductive effects in pups born to these rats. Decreased body weight was found during lactation and the early post-weaning phase in pups nursed by dams given the highest dose used (6 mg/kg/day, equivalent to an adult human dose of 160 mg/day, on a mg/m^2 basis). However, body weight of these pups recovered. In published studies, offspring of pregnant rats administered oxycodone hydrochloride during gestation have been reported to exhibit neurobehavioral effects including altered stress responses and increased anxiety-like behavior (2 mg/kg/day IV from Gestation Day 8 to 21 and Postnatal Day 1, 3, and 5; 0.3-times an adult human oral dose of 60 mg/day on a mg/m^2 basis), and altered learning and memory (15 mg/kg/day orally from breeding through parturition; 2.4 times an adult human oral dose of 60 mg/day on a mg/m^2 basis).

8.2 Lactation

Risk Summary

Oxycodone is present in breast milk. Published lactation studies report variable concentrations of oxycodone in breast milk with administration of immediate-release oxycodone to nursing mothers in the early postpartum period. The lactation studies did not assess breastfed infants for potential adverse reactions. Lactation studies have not been conducted with extended–release oxycodone, including XTAMPZA ER, and no information is available on the effects of the drug on the breastfed infant or the effects of the drug on milk production. Because of the potential for serious adverse reactions, including excess sedation and respiratory depression in a breastfed infant, advise patients that breastfeeding is not recommended during treatment with XTAMPZA ER.

Clinical Considerations

Monitor infants exposed to XTAMPZA ER through breast milk for excess sedation and respiratory depression. Withdrawal symptoms can occur in breastfed infants when maternal administration of an opioid analgesic is stopped, or when breast-feeding is stopped.

8.3 Females and Males of Reproductive Potential

Infertility

Use of opioids for an extended period of time may cause reduced fertility in females and males of reproductive potential. It is not known whether these effects on fertility are reversible [see Adverse Reactions (6.2), Clinical Pharmacology (12.2), Nonclinical Toxicology (13.1)].

8.4 Pediatric Use

Safety and effectiveness of XTAMPZA ER in pediatric patients below the age of 18 years have not been established.

8.5 Geriatric Use

In controlled pharmacokinetic studies in elderly subjects (greater than 65 years) the clearance of oxycodone was slightly reduced. Compared to young adults, the plasma concentrations of oxycodone were increased approximately 15% [see Clinical Pharmacology (12.3)]. Of the total number of subjects entered into the titration phase of the Phase 3 study for XTAMPZA ER (740), 88 (12%) were age 65 and older. In this clinical trial with appropriate initiation of therapy and dose titration, no untoward or unexpected adverse reactions were seen in the elderly patients who received XTAMPZA ER. Thus, the usual doses and dosing intervals may be appropriate for elderly patients. Use caution when selecting a dosage for an elderly patient, usually starting at the low end of the dosing range, reflecting the greater frequency of decreased hepatic, renal, or cardiac function, concomitant disease, and use of other drug therapy.

Respiratory depression is the chief risk in elderly patients treated with opioids and has occurred after large initial doses were administered to patients who were not opioid-tolerant or when opioids were co-administered with other agents that depress respiration. Titrate the dosage of XTAMPZA ER slowly in geriatric patients and frequently reevaluate the patient for signs of central nervous system and respiratory depression [see Warnings and Precautions (5.8)].

8.6 Hepatic Impairment

A study in patients with hepatic impairment demonstrated greater plasma oxycodone concentrations than those seen at equivalent doses in persons with normal hepatic function. A similar effect on plasma oxycodone concentrations can be expected for patients with hepatic impairment taking XTAMPZA ER. Therefore, in the setting of hepatic impairment, start dosing patients at 1/3 to 1/2 the usual starting dose followed by careful dose titration. Use of alternative analgesics is recommended for patients who require a dose of XTAMPZA ER less than 9 mg [see Dosage and Administration (2.4), Clinical Pharmacology (12.3)].

8.7 Renal Impairment

In patients with renal impairment, as evidenced by decreased creatinine clearance (<60 mL/min), the concentrations of oxycodone in the plasma are approximately 50% higher than in subjects with normal renal function. Follow a conservative approach to dose initiation and adjust according to the clinical situation. Use of alternative analgesics is recommended for patients who require a dose of XTAMPZA ER less than 9 mg [see Clinical Pharmacology (12.3)].

8.8 Sex Differences

In pharmacokinetic studies with XTAMPZA ER, healthy female subjects demonstrate up to 20% higher oxycodone plasma exposures than males, even after considering differences in body weight or BMI. The clinical relevance of a difference of this magnitude is low for a drug intended for chronic usage at individualized dosages. In the Phase 3 clinical trial there was a greater frequency of typical opioid adverse events for females than males; there was no male/female difference detected for efficacy.

9 DRUG ABUSE AND DEPENDENCE

9.1 Controlled Substance

XTAMPZA ER contains oxycodone, a Schedule II controlled substance.

9.2 Abuse

XTAMPZA ER contains oxycodone, a substance with high potential for misuse and abuse, which can lead to the development of substance use disorder, including addiction [see Warnings and Precautions (5.1)].

Misuse is the intentional use, for therapeutic purposes, of a drug by an individual in a way other than prescribed by a healthcare provider or for whom it was not prescribed.

Abuse is the intentional, non-therapeutic use of a drug, even once, for its desirable psychological or physiological effects.

Drug addiction is a cluster of behavioral, cognitive, and physiological phenomena that may include a strong desire to take the drug, difficulties in controlling drug use (e.g., continuing drug use despite harmful consequences, giving a higher priority to drug use than other activities and obligations), and possible tolerance or physical dependence.

Misuse and abuse of XTAMPZA ER increases risk of overdose, which may lead to central nervous system and respiratory depression, hypotension, seizures, and death. The risk is increased with concurrent abuse of XTAMPZA ER with alcohol and/or other CNS depressants. Abuse of and addiction to opioids in some individuals may not be accompanied by concurrent tolerance and symptoms of physical dependence. In addition, abuse of opioids can occur in the absence of addiction.

All patients treated with opioids require careful and frequent reevaluation for signs of misuse, abuse, and addiction, because use of opioid analgesic products carries the risk of addiction even under appropriate medical use. Patients at high risk of XTAMPZA ER abuse include those with a history of prolonged use of any opioid, including products containing buprenorphine, those with a history of drug or alcohol abuse, or those who use XTAMPZA ER in combination with other abused drugs.

"Drug-seeking" behavior is very common in persons with substance use disorders. Drug-seeking tactics include emergency calls or visits near the end of office hours, refusal to undergo appropriate examination, testing, or referral, repeated "loss" of prescriptions, tampering with prescriptions, and reluctance to provide prior medical records or contact information for other treating healthcare provider(s). "Doctor shopping" (visiting multiple prescribers to obtain additional prescriptions) is common among people who abuse drugs and people with substance use disorder. Preoccupation with achieving adequate pain relief can be appropriate behavior in a patient with inadequate pain control.

XTAMPZA ER, like other opioids, can be diverted for nonmedical use into illicit channels of distribution. Careful record-keeping of prescribing information, including quantity, frequency, and renewal requests, as required by state and federal law, is strongly advised.

Proper assessment of the patient, proper prescribing practices, periodic reevaluation of therapy, and proper dispensing and storage are appropriate measures that help to limit abuse of opioid drugs.

Risks Specific to Abuse of XTAMPZA ER

Abuse of XTAMPZA ER poses a risk of overdose and death. The risk is increased with concurrent use of XTAMPZA ER with alcohol and/or other CNS depressants [see Warnings and Precautions (5.1, 5.3), Drug Interactions (7)].

XTAMPZA ER is approved for oral use only.

Parenteral drug abuse is commonly associated with transmission of infectious diseases such as hepatitis and HIV.

Abuse Deterrence Studies

XTAMPZA ER capsules contain microspheres formulated with inactive ingredients intended to make the formulation more difficult to manipulate for misuse and abuse.

In Vitro Testing

In vitro physical and chemical manipulation studies were performed to evaluate the success of different methods of defeating the extended-release formulation.

Results support that, relative to immediate-release oxycodone tablets, XTAMPZA ER is less susceptible to the effects of grinding, crushing, and extraction using a variety of tools and solvents.

XTAMPZA ER resisted attempts to pass the melted capsule contents or the microspheres suspended in water through a hypodermic needle.

Pharmacokinetic Studies

The pharmacokinetic profile of manipulated XTAMPZA ER capsule contents (36 mg; [equivalent to 40 mg oxycodone HCl]) was characterized following oral (three studies) and intranasal (two studies) administration. The studies were conducted in a randomized, cross-over design. In studies assessing manipulation by crushing, the most effective crushing method identified in previous in vitro studies was applied to the product(s).

Oral Pharmacokinetic Studies, Manipulated and Intact XTAMPZA ER

The effect of two types of product manipulation (crushing and chewing) on XTAMPZA ER pharmacokinetics was measured in three studies.

In one oral pharmacokinetic study, XTAMPZA ER capsule contents were crushed or chewed prior to oral administration in healthy, naltrexone-blocked volunteers. The two comparators in this study were intact XTAMPZA ER capsules and an immediate-release solution of oxycodone at an equivalent dose.

In two oral pharmacokinetic studies, XTAMPZA ER capsule contents were crushed prior to oral administration in healthy, naltrexone-blocked volunteers. The comparators in these studies included intact XTAMPZA ER capsules, intact and crushed reformulated OXYCONTIN (oxycodone hydrochloride) extended-release tablets at an equivalent dose, and crushed immediate-release oxycodone tablets at an equivalent dose.

The data displayed in Table 4 illustrate the findings from the oral pharmacokinetic studies (data were similar for the two oral pharmacokinetic studies comparing XTAMPZA ER to OXYCONTIN). Collectively, the data demonstrated that crushing or chewing XTAMPZA ER prior to administration did not increase the maximum observed plasma concentration (Cmax) or total exposure (AUC0-INF) relative to dosing the intact product under fed conditions. Relative to immediate-release oxycodone and crushed reformulated OXYCONTIN (oxycodone hydrochloride) extended-release tablets, the Cmax for all XTAMPZA ER treatments was lower and the Tmax longer, consistent with an extended-release profile.

Table 4: Oxycodone Pharmacokinetic Parameters, Administration of Manipulated and Intact Dosage Forms (36 mg of XTAMPZA ER or equivalent)
 | Cmax (ng/mL) | Tmax (hr) | AUC0-INF (hr∙ng/mL)
Treatment | Oral Pharmacokinetic Study 1
Intact XTAMPZA ER Capsules (fed) | 62.3 (13.0) | 4.0 (1.5-6) | 561 (124)
Crushed XTAMPZA ER Capsule Contents (fed) | 57.6 (12.6) | 4.5 (2.5-6) | 553 (134)
Chewed XTAMPZA ER Capsule Contents (fed) | 55.6 (10.9) | 4.5 (2.5-8) | 559 (113)
Immediate-Release Oxycodone Solution (fasted) | 115 (27.3) | 0.75 (0.5-2) | 489 (80.2)
 | Oral Pharmacokinetic Study 2
Intact XTAMPZA ER Capsules (fed) | 67.5 (17.6) | 3.5 (1.25-6.0) | 581 (138)
Crushed XTAMPZA ER Capsule Contents (fed) | 62.9 (12.6) | 4.0 (2.0-7.0) | 597 (149)
Intact reformulated OXYCONTIN (oxycodone hydrochloride) extended-release tablets (fed) | 64.9 (13.8) | 5.0 (2.0-10.0) | 611 (145)
Crushed reformulated OXYCONTIN (oxycodone hydrochloride) extended-release tablets (fed) | 78.4 (12.9) | 1.75 (0.5-5.0) | 587 (132)
Crushed Immediate-Release Oxycodone Tablets (fed) | 79.4 (17.1) | 1.75 (0.5-4.0) | 561 (146)
Values shown for Cmax and AUC0-INF are mean (standard deviation); values shown for Tmax are median (minimum-maximum).

Nasal Pharmacokinetic Studies

The pharmacokinetic profile following intranasal administration of crushed XTAMPZA ER capsule contents was characterized in two clinical studies.

In Nasal Pharmacokinetic Study 1, XTAMPZA ER capsule contents (36 mg) were crushed and intranasally administered by non-dependent, naltrexone-blocked subjects with a history of nasal abuse of opioids. The two comparators in this study were intact XTAMPZA ER capsules (oral) and oxycodone HCl powder (intranasal) at an equivalent dose.

In Nasal Pharmacokinetic Study 2, XTAMPZA ER capsule contents (36 mg) were crushed and intranasally administered by non-dependent subjects with a history of nasal abuse of opioids. The two comparators in this study were intact XTAMPZA ER capsules (oral) and crushed oxycodone immediate-release tablets (intranasal) at an equivalent dose.

The results of Nasal Pharmacokinetic Studies 1 and 2 are comparable and both studies demonstrated that intranasal administration of crushed XTAMPZA ER capsule contents did not result in higher peak plasma concentration (Cmax) or shorter time to peak concentration (Tmax) than taking XTAMPZA ER orally. The data from Nasal Pharmacokinetic Study 2 are displayed in Table to represent these findings.

Table 5: Oxycodone Pharmacokinetic Parameters, Nasal Pharmacokinetic Study 2:
Treatment | Cmax (ng/mL) | Tmax (hr) | AUC0-INF (hr∙ng/mL)
Intact XTAMPZA ER Capsules (oral) | 41.0 (10.0) | 5.1 (1.6-8.1) | 477 (89.6)
Crushed XTAMPZA ER Capsule Contents (nasal) | 29.8 (6.6) | 5.1 (1.6-12.1) | 459 (106)
Crushed Immediate-Release Tablets (nasal) | 60.9 (11.9) | 2.6 (0.3-6.1) | 577 (124)
Values shown for Cmax and AUC0-INF are mean (standard deviation); values shown for Tmax are median (minimum-maximum).

Clinical Studies

Oral Abuse Potential Studies:

The oral abuse potential of chewed XTAMPZA ER was evaluated in two studies.

In a randomized, double-blind, active- and placebo-controlled, single-dose, six-way crossover pharmacodynamic study, 52 non-dependent recreational opioid users received orally-administered active and placebo treatment. The six treatment arms were intact XTAMPZA ER (36 mg, fed and fasted); chewed XTAMPZA ER (36 mg, fed and fasted); crushed immediate-release (IR) oxycodone HCl in solution (40 mg, fasted, equivalent to 36 mg of XTAMPZA ER), and placebo. Data for chewed and intact XTAMPZA ER and crushed IR oxycodone in the fasted state are described below.

Drug Liking was measured on a bipolar 100-point Visual Analog Scale (VAS) where 50 represents a neutral response, 0 represents maximum disliking, and 100 represents maximum liking. Response to whether the subject would take the study drug again was also measured on a bipolar 100-point VAS where 50 represents a neutral response, 0 represents the strongest negative response (e.g., 'definitely would not take drug again'), and 100 represents the strongest positive response (e.g., 'definitely would take drug again').

Fifty-two subjects completed the study, and the results are summarized in Table 5. The oral administration of chewed and intact XTAMPZA ER in the fasted state was associated with statistically lower mean Drug Liking and Take Drug Again VAS scores compared with crushed immediate-release oxycodone. In addition, the Drug Liking and Take Drug Again scores were similar for XTAMPZA ER taken in the intact and chewed states.

Table 6: Summary of Maximum Drug Liking and Take Drug Again (Emax) Following Oral Administration
 |  | XTAMPZA ER Intact (Fasted) | XTAMPZA ER Chewed (Fasted) | Crushed IR Oxycodone (Fasted) | Placebo
Drug Liking [Bipolar scale (0=maximum negative response, 50=neutral response, 100=maximum positive response)] (Emax) | Mean (SD) | 73.9 (15.10) | 73.3 (14.93) | 86.40 (12.01) | 55.8 (9.94)
Drug Liking [Bipolar scale (0=maximum negative response, 50=neutral response, 100=maximum positive response)] (Emax) | Median (Range) | 73.5 (50-100) | 73.5 (50-100) | 88.5 (52-100) | 50.0 (50-86)
Take Drug Again (Emax) | Mean (SD) | 77.98 (21.07) | 77.85 (18.30) | 87.69 (12.90) | 50.79 (21.41)
Take Drug Again (Emax) | Median (Range) | 80.5 (1-100) | 81.5 (50-100) | 90.5 (50-100) | 50.0 (0-100)
Emax = maximum (peak) effect; ER = extended-release; IR = immediate-release; VAS = visual analogue scale; SD=Standard Deviation.

A prior, similarly-designed study was also conducted to evaluate the oral abuse potential of chewed XTAMPZA ER. Although the oral administration of chewed and intact XTAMPZA ER in the fasted state was associated with statistically lower mean Drug Liking scores compared with crushed immediate-release oxycodone, the results for Take Drug Again showed small differences that were not statistically significant.

Nasal Abuse Potential Study:

In a randomized, double-blind, active- and placebo-controlled, single-dose, four-way crossover pharmacodynamic study, 39 recreational opioid users with a history of intranasal drug abuse received nasally administered active and placebo drug treatment. The four treatment arms were crushed XTAMPZA ER 36 mg dosed intranasally; intact XTAMPZA ER 36 mg dosed orally; crushed immediate-release oxycodone HCl 40 mg (equivalent to 36 mg of XTAMPZA ER) dosed intranasally; and placebo. Data for intranasal XTAMPZA ER and crushed immediate-release oxycodone are described below.

Thirty-six subjects completed the study. Intranasal administration of crushed XTAMPZA ER was associated with statistically lower mean Drug Liking and Take Drug Again scores compared with crushed immediate-release oxycodone (summarized in 7).

Table 7: Summary of Maximum Drug Liking and Take Drug Again (Emax) Following Intranasal Administration
 |  | XTAMPZA ER Intranasal | Crushed IR Oxycodone Intranasal | Placebo
Drug Liking [Bipolar scale (0=maximum negative response, 50=neutral response, 100=maximum positive response).] (Emax) | Mean (SD) | 61.81 (15.64) | 82.72 (10.95) | 54.5 (11.77)
Drug Liking [Bipolar scale (0=maximum negative response, 50=neutral response, 100=maximum positive response).] (Emax) | Median (Range) | 59.5 (16-94) | 84 (60-100) | 51 (28-93)
Take Drug Again (Emax) | Mean (SD) | 47.67 (27.84) | 71.36 (23.49) | 45.92 (17.50)
Take Drug Again (Emax) | Median (Range) | 50 (0-100) | 78.5 (18-100) | 50 (0-97)
Emax = maximum (peak) effect; ER = extended-release; IR = immediate-release; VAS = visual analogue scale; SD=Standard Deviation.

Figure 1 demonstrates a comparison of Drug Liking for intranasal administration of crushed XTAMPZA ER compared to crushed immediate-release oxycodone in subjects who received both treatments (N=36). The Y-axis represents the percent of subjects attaining a percent reduction in drug liking for XTAMPZA ER vs. immediate-release oxycodone greater than or equal to the value on the X-axis. Approximately 92% (n = 33) of subjects had some reduction in drug liking with XTAMPZA ER relative to crushed immediate-release oxycodone HCl. Approximately 78% (n = 28) of subjects had a reduction of at least 30% in drug liking with XTAMPZA ER compared to crushed immediate-release oxycodone HCl, and approximately 58% (n = 21) of subjects had a reduction of at least 50% in drug liking with XTAMPZA ER compared to crushed immediate-release oxycodone HCl.

Figure 1: Percent Reduction Profiles for Emax of Drug Liking VAS for Crushed XTAMPZA ER vs. Crushed Immediate-release Oxycodone, N=36 Following Intranasal Administration

Summary

The in vitro data demonstrate that XTAMPZA ER has physicochemical properties expected to make abuse by injection difficult. The data from pharmacokinetic and human abuse potential studies, along with support from the in vitro data, also indicate that XTAMPZA ER has physicochemical properties that are expected to reduce abuse via the oral and intranasal routes. The data from the oral pharmacokinetic studies of crushed or chewed XTAMPZA ER demonstrated a lack of dose dumping with no increase in oxycodone levels compared to intact XTAMPZA ER.

However, abuse of XTAMPZA ER by injection and by the oral and nasal routes of administration is still possible.

Additional data, including epidemiological data, when available, may provide further information on the impact of the current formulation of XTAMPZA ER on the abuse liability of the drug. Accordingly, this section may be updated in the future as appropriate.

XTAMPZA ER contains oxycodone, an opioid agonist and Schedule II controlled substance with an abuse liability similar to other opioid agonists, legal or illicit, including fentanyl, hydromorphone, methadone, morphine, and oxymorphone. XTAMPZA ER can be abused and is subject to misuse, addiction, and criminal diversion [see Warnings and Precautions (5.1) and Drug Abuse and Dependence (9.3)].

9.3 Dependence

Both tolerance and physical dependence can develop during use of opioid therapy.

Tolerance is a physiological state characterized by a reduced response to a drug after repeated administration (i.e., a higher dose of a drug is required to produce the same effect that was once obtained at a lower dose).

Physical dependence is a state that develops as a result of a physiological adaptation in response to repeated drug use, manifested by withdrawal signs and symptoms after abrupt discontinuation or a significant dose reduction of a drug.

Withdrawal may be precipitated through the administration of drugs with opioid antagonist activity (e.g., naloxone, nalmefene), mixed agonist/antagonist analgesics (e.g., pentazocine, butorphanol, nalbuphine), or partial agonists (e.g., buprenorphine). Physical dependence may not occur to a clinically significant degree until after several days to weeks of continued use.

Do not rapidly reduce or abruptly discontinue XTAMPZA ER in a patient physically dependent on opioids. Rapid tapering of XTAMPZA ER in a patient physically dependent on opioids may lead to serious withdrawal symptoms, uncontrolled pain, and suicide. Rapid discontinuation has also been associated with attempts to find other sources of opioid analgesics, which may be confused with drug-seeking for abuse.

When discontinuing XTAMPZA ER, gradually taper the dosage using a patient-specific plan that considers the following: the dose of XTAMPZA ER the patient has been taking, the duration of treatment, and the physical and psychological attributes of the patient. To improve the likelihood of a successful taper and minimize withdrawal symptoms, it is important that the opioid tapering schedule is agreed upon by the patient. In patients taking opioids for an extended period of time at high doses, ensure that a multimodal approach to pain management, including mental health support (if needed), is in place prior to initiating an opioid analgesic taper [see Dosage and Administration (2.6), Warnings and Precautions (5.14)].

Infants born to mothers physically dependent on opioids will also be physically dependent and may exhibit respiratory difficulties and withdrawal signs [see Use in Specific Populations (8.1)].

10 OVERDOSAGE

Clinical Presentation

Acute overdosage with oxycodone can be manifested by respiratory depression, somnolence progressing to stupor or coma, skeletal muscle flaccidity, cold and clammy skin, constricted pupils, and, in some cases, pulmonary edema, bradycardia, hypotension, hypoglycemia, partial or complete airway obstruction, atypical snoring, and death. Marked mydriasis rather than miosis may be seen due to severe hypoxia in overdose situations [see Clinical Pharmacology (12.2)]. Toxic leukoencephalopathy has been reported after opioid overdose and can present hours, days, or weeks after apparent recovery from the initial intoxication.

Treatment of Overdose

In case of overdose, priorities are the reestablishment of a patent and protected airway and institution of assisted or controlled ventilation if needed. Employ other supportive measures (including oxygen, vasopressors) in the management of circulatory shock and pulmonary edema as indicated. Cardiac arrest or arrhythmias will require advanced life-support measures.

For clinically significant respiratory or circulatory depression secondary to oxycodone overdose, administer an opioid overdose reversal agent such as naloxone or nalmefene.

Because the duration of reversal would be expected to be less than the duration of action of oxycodone in XTAMPZA ER, carefully monitor the patient until spontaneous respiration is reliably reestablished. XTAMPZA ER will continue to release oxycodone and add to the oxycodone load for 24 to 48 hours or longer following ingestion necessitating prolonged monitoring. If the response to opioid overdose reversal agent is suboptimal or only brief in nature, administer additional reversal agent as directed in the product's prescribing information.

In an individual physically dependent on opioids, administration of the usual dosage of the opioid overdose reversal agent will precipitate an acute withdrawal syndrome. The severity of the withdrawal symptoms experienced will depend on the degree of physical dependence and the dose of the reversal agent administered. If a decision is made to treat serious respiratory depression in the physically dependent patient, administration of the reversal agent should be begun with care and by titration with smaller than usual doses of the reversal agent.

11 DESCRIPTION

XTAMPZA ER (oxycodone) extended-release capsules are an opioid agonist for oral use. The capsules contain microspheres formulated with oxycodone base and are supplied in strengths of 9 mg (equivalent to 10 mg oxycodone HCl), 13.5 mg (equivalent to 15 mg oxycodone HCl), 18 mg (equivalent to 20 mg oxycodone HCl), 27 mg (equivalent to 30 mg oxycodone HCl), and 36 mg (equivalent to 40 mg oxycodone HCl) capsules. The capsule strengths describe the amount of oxycodone base per capsule. The structural formula for oxycodone is as follows:

C18H21NO4 MW 315.37 g/mol

The chemical name is 4,5 α-Epoxy-14-hydroxy-3-methoxy-17-methylmorphinan-6-one.

Oxycodone base is a white, odorless crystalline powder derived from the opium alkaloid, thebaine. Oxycodone is present as myristate salt in the XTAMPZA ER formulation.

Each XTAMPZA ER capsule contains either 9, 13.5, 18, 27, or 36 mg of oxycodone (equivalent to 10, 15, 20, 30, or 40 mg of oxycodone HCl, respectively) and the following inactive ingredients: myristic acid, yellow beeswax, carnauba wax, stearoyl polyoxyl-32 glycerides, magnesium stearate, and colloidal silicon dioxide. The capsule shells collectively contain titanium dioxide, hypromellose, and water. Additionally, the 9 mg and 18 mg strength capsule shells contain yellow iron oxide, the 13.5 and 36 mg strength capsule shells contain red iron oxide, and the 27 mg strength capsule shells contain black iron oxide.

12 CLINICAL PHARMACOLOGY

12.1 Mechanism of Action

Oxycodone is a full opioid agonist and is relatively selective for the mu receptor, although it can bind to other opioid receptors at higher doses. The principal therapeutic action of oxycodone is analgesia. Like all full opioid agonists, there is no ceiling effect to analgesia for oxycodone. Clinically, dosage is titrated to provide adequate analgesia and may be limited by adverse reactions, including respiratory and CNS depression.

The precise mechanism of the analgesic action is unknown. However, specific CNS opioid receptors for endogenous compounds with opioid-like activity have been identified throughout the brain and spinal cord and are thought to play a role in the analgesic effects of this drug. In addition, when oxycodone binds to mu-opioid receptors, it results in positive subjective effects, such as drug liking, euphoria, and high.

12.2 Pharmacodynamics

Effects on the Central Nervous System

Oxycodone produces respiratory depression by direct action on brain stem respiratory centers. The respiratory depression involves a reduction in the responsiveness of the brain stem respiratory centers to both increases in CO2 tension and to electrical stimulation.

Oxycodone causes miosis, even in total darkness. Pinpoint pupils are a sign of opioid overdose but are not pathognomonic (e.g., pontine lesions of hemorrhagic or ischemic origin may produce similar findings). Marked mydriasis rather than miosis may be seen due to hypoxia in overdose situations [see Overdosage (10)].

Effects on the Gastrointestinal Tract and Other Smooth Muscle

Oxycodone causes a reduction in motility associated with an increase in smooth muscle tone in the antrum of the stomach and duodenum. Digestion of food in the small intestine is delayed and propulsive contractions are decreased. Propulsive peristaltic waves in the colon are decreased, while tone may be increased to the point of spasm resulting in constipation. Other opioid-induced effects may include a reduction in biliary and pancreatic secretions, spasm of sphincter of Oddi, transient elevations in serum amylase, and opioid-induced esophageal dysfunction (OIED).

Effects on the Cardiovascular System

Oxycodone produces peripheral vasodilation which may result in orthostatic hypotension or syncope. Manifestations of histamine release and/or peripheral vasodilation may include pruritus, flushing, red eyes and sweating and/or orthostatic hypotension.

Effects on the Endocrine System

Opioids inhibit the secretion of adrenocorticotropic hormone (ACTH), cortisol, and luteinizing hormone (LH) in humans [see Adverse Reactions (6.2)]. They also stimulate prolactin, growth hormone (GH) secretion, and pancreatic secretion of insulin and glucagon.

Use of opioids for an extended period of time may influence the hypothalamic-pituitary-gonadal axis, leading to androgen deficiency that may manifest as low libido, impotence, erectile dysfunction, amenorrhea, or infertility. The causal role of opioids in the clinical syndrome of hypogonadism is unknown because the various medical, physical, lifestyle, and psychological stressors that may influence gonadal hormone levels have not been adequately controlled for in studies conducted to date [see Adverse Reactions (6.2)].

Effects on the Immune System

Opioids have been shown to have a variety of effects on components of the immune system in in vitro and animal models. The clinical significance of these findings is unknown. Overall, the effects of opioids appear to be modestly immunosuppressive.

Concentration–Efficacy Relationships

Studies in normal volunteers and patients reveal predictable relationships between oxycodone dosage and plasma oxycodone concentrations, as well as between concentration and certain expected opioid effects, such as pupillary constriction, sedation, overall subjective "drug effect," analgesia, and feelings of relaxation.

The minimum effective analgesic concentration will vary widely among patients, especially among patients who have been previously treated with opioid agonists. The minimum effective analgesic concentration of oxycodone for any individual patient may increase over time due to an increase in pain, the development of a new pain syndrome, and/or the development of analgesic tolerance [see Dosage and Administration (2.1, 2.5)].

Concentration–Adverse Reaction Relationships

There is a relationship between increasing oxycodone plasma concentration and increasing frequency of dose-related opioid adverse reactions such as nausea, vomiting, CNS effects, and respiratory depression. In opioid-tolerant patients, the situation may be altered by the development of tolerance to opioid-related adverse reactions.

12.3 Pharmacokinetics

The activity of XTAMPZA ER is primarily due to the parent drug oxycodone. XTAMPZA ER is designed to provide delivery of oxycodone over 12 hours.

Absorption

XTAMPZA ER is not bioequivalent to oxycodone extended-release tablets. In the fasted state, both peak serum concentration (Cmax) and extent of absorption (AUC) are lower for XTAMPZA ER, and in the fed state, Cmax is lower, but AUC is similar.

Compared to immediate-release oxycodone solution dosed under fasted conditions the mean Cmax of oxycodone from XTAMPZA ER is lower (73% and 43% lower for fasted and fed administration, respectively) and the median time to peak plasma concentration (Tmax) is approximately 3 hours longer. The extent of absorption of oxycodone from XTAMPZA ER is less than from immediate-release oxycodone oral solution in the fasted state (relative bioavailability of 75%), but comparable in the fed state (relatively bioavailability of 114%).

The peak plasma concentration of oxycodone from XTAMPZA ER occurs approximately 4.5 hours after fed dose administration. Upon repeated dosing with XTAMPZA ER in healthy subjects in pharmacokinetic studies, steady-state levels were achieved within 24-36 hours. Oxycodone is extensively metabolized and eliminated primarily in the urine as both conjugated and unconjugated metabolites. The apparent elimination half-life (t½) of oxycodone following the administration of XTAMPZA ER when dosed in the fed state was 5.6 hours compared to 3.2 hours for immediate-release oxycodone.

Food Effects

The oral bioavailability of oxycodone from XTAMPZA ER is greater when taken with food than when taken in the fasted state. The oral bioavailability is dependent on the food consumed and is greatest following a high-fat and high-calorie meal with an increase in Cmax of 100-150% and AUC of 50-60% compared to the fasted state. Following a medium-fat medium-calorie meal, the Cmax increased by 84% and AUC by 28% compared to the fasted state. Following a low-fat low-calorie meal, Cmax was 19% higher and AUC was comparable, relative to the fasted state.

Pharmacokinetic Profile of XTAMPZA ER Intact and Sprinkled

Plasma concentration over time has been measured following administration of XTAMPZA ER capsule contents intact with food and sprinkled. The pharmacokinetic profile for the capsule contents sprinkled was equivalent to intact capsule administration (Table 8).

Table 8: Oxycodone Pharmacokinetic Parameters, Administration of Capsule Contents and Intact Capsules (36 mg)
Treatment | Cmax (ng/mL) | Tmax (hr) | AUC0-INF (hr∙ng/mL)
Intact XTAMPZA ER Capsules (fed) | 55.3 (13.6) | 4.5 (1.5 – 9.0) | 540 (143)
Sprinkled XTAMPZA ER Capsule Contents (fed) | 48.1 (12.0) | 4.5 (2.5 – 9.0) | 528 (130)
Values shown for Cmax and AUC0-INF are mean (standard deviation); values shown for Tmax are median (minimum – maximum).

Distribution

Following intravenous administration, the steady-state volume of distribution (Vss) for oxycodone was 2.6 L/kg. Oxycodone binding to plasma protein at 37°C and a pH of 7.4 was about 45%. Once absorbed, oxycodone is distributed to skeletal muscle, liver, intestinal tract, lungs, spleen, and brain. Oxycodone has been found in breast milk [see Use in Specific Populations (8.2)].

Elimination

In humans, oxycodone is extensively metabolized. Oxycodone and its metabolites are excreted primarily via the kidney.

Metabolism

Oxycodone is extensively metabolized by multiple metabolic pathways to produce noroxycodone, oxymorphone, and noroxymorphone, which are subsequently glucuronidated. Noroxycodone and noroxymorphone are the major circulating metabolites. CYP3A mediated N-demethylation to noroxycodone is the primary metabolic pathway of oxycodone with a lower contribution from CYP2D6-mediated O-demethylation to oxymorphone. Therefore, the formation of these and related metabolites can, in theory, be affected by other drugs [see Drug Interactions (7)].

Noroxycodone exhibits very weak anti-nociceptive potency compared to oxycodone; however, it undergoes further oxidation to produce noroxymorphone, which is active at opioid receptors. Although noroxymorphone is an active metabolite and present at relatively high concentrations in circulation, it does not appear to cross the blood-brain barrier to a significant extent. Oxymorphone is present in the plasma only at low concentrations and undergoes further metabolism to form its glucuronide and noroxymorphone. Oxymorphone has been shown to be active and to possess analgesic activity but its contribution to analgesia following oxycodone administration is thought to be clinically insignificant. Other metabolites (α- and ß-oxycodol, noroxycodol, and oxymorphol) may be present at very low concentrations and demonstrate limited penetration into the brain as compared to oxycodone. The enzymes responsible for keto-reduction and glucuronidation pathways in oxycodone metabolism have not been established.

Excretion

Oxycodone and its metabolites are excreted primarily via the kidney. The amounts measured in the urine have been reported as follows: free and conjugated oxycodone 8.9%, free noroxycodone 23%, free oxymorphone less than 1%, conjugated oxymorphone 10%, free and conjugated noroxymorphone 14%, reduced free and conjugated metabolites up to 18%. The total plasma clearance was approximately 1.4 L/min in adults.

Specific Populations

Age: Geriatric Population

The plasma concentrations of oxycodone are nominally affected by age, being 15% greater in elderly as compared to young subjects (age 21-45).

Sex

Across individual pharmacokinetic studies, oxycodone plasma exposures for female subjects were up to 20% higher than for male subjects, even after considering differences in body weight or BMI. The reason for this difference is unknown [see Use in Specific Populations (8)].

Renal Impairment

Data from a pharmacokinetic study involving 13 patients with mild to severe renal dysfunction (creatinine clearance <60 mL/min) showed peak plasma oxycodone and noroxycodone concentrations 50% and 20% higher, respectively, and AUC values for oxycodone, noroxycodone, and oxymorphone 60%, 50%, and 40% higher than normal subjects, respectively. This was accompanied by an increase in sedation, but not by differences in respiratory rate, pupillary constriction, or several other measures of drug effect. There was an increase in mean elimination t½ for oxycodone of 1 hour.

Hepatic Impairment

Data from a study involving 24 patients with mild to moderate hepatic dysfunction show peak plasma oxycodone and noroxycodone concentrations 50% and 20% higher, respectively, than healthy subjects. AUC values are 95% and 65% higher, respectively. Oxymorphone peak plasma concentrations and AUC values are lower by 30% and 40%. The mean elimination t½ for oxycodone increased by 2.3 hours.

Drug Interaction Studies

CYP3A4 Inhibitors

CYP3A4 is the major enzyme involved in noroxycodone formation. Co-administration of a 10 mg single dose of oxycodone extended –release tablet and the CYP3A4 inhibitor ketoconazole (200 mg BID) increased oxycodone AUC and Cmax by 170% and 100%, respectively [see Drug Interactions (7)].

CYP3A4 Inducers

A published study showed that the co-administration of rifampin, a drug metabolizing enzyme inducer, decreased oxycodone AUC and Cmax values by 86% and 63%, respectively [see Drug Interactions (7)].

CYP2D6 Inhibitors

Oxycodone is metabolized in part to oxymorphone via CYP2D6. While this pathway may be blocked by a variety of drugs such as certain cardiovascular drugs (e.g., quinidine) and antidepressants (e.g., fluoxetine), such blockade is not expected to be of clinical significance for XTAMPZA ER [see Drug Interactions (7)].

13 NONCLINICAL TOXICOLOGY

13.1 Carcinogenesis, Mutagenesis, Impairment of Fertility

Carcinogenesis

Long term studies in animals to evaluate the carcinogenic potential of oxycodone have not been conducted.

Mutagenesis

Oxycodone was genotoxic in the in vitro mouse lymphoma assay. Oxycodone was negative when tested at appropriate concentrations in the in vitro chromosomal aberration assay, the in vitro bacterial reverse mutation assay (Ames test), and the in vivo bone marrow micronucleus assay in mice.

Impairment of Fertility

In a study of reproductive performance, rats were administered a once daily gavage dose of the vehicle or oxycodone hydrochloride (0.5, 2, and 8 mg/kg). Male rats were dosed for 28 days before cohabitation with females, during the cohabitation and until necropsy (2-3 weeks post-cohabitation). Females were dosed for 14 days before cohabitation with males, during cohabitation and up to Gestation Day 6. Oxycodone HCl did not affect reproductive function in male or female rats at any dose tested (≤8 mg/kg/day), up to 1.3 times a human dose of 60 mg/day.

13.2 Animal Toxicology

The safety of beeswax, carnauba wax, and myristic acid in XTAMPZA ER in doses exceeding a total daily dose of 288 mg oxycodone per day (equivalent to 320 mg oxycodone HCl per day) has not been studied.

14 CLINICAL STUDIES

An enriched-enrollment, randomized-withdrawal, double-blind, placebo-controlled, parallel group, study was conducted in 740 patients with persistent, moderate-to-severe chronic lower back pain, with inadequate pain control from their prior therapy. During screening, patients stopped their prior opioid analgesics and/or non-opioid analgesics prior to starting XTAMPZA ER treatment. Patients were titrated to a stable and tolerated dose between 18 mg (equivalent to 20 mg oxycodone HCl) twice daily and 72 mg (equivalent to 80 mg oxycodone HCl) twice daily of XTAMPZA ER in an open-label fashion during the first six weeks of the trial. Optional use of rescue medication (acetaminophen 500 mg tablets) up to 2 tablets every 4-6 hours was permitted during the dose titration phase, up to 2000 mg per day. XTAMPZA ER was titrated once every three to seven days until a stable and tolerable dose was identified (maximum dose of 72 mg [equivalent to 80 mg oxycodone HCl] twice daily).

Following the titration phase, 389 subjects (53%) met the study randomization criteria of adequate analgesia (pain reduction of at least 2 points from screening baseline to a score of 4 or less on a 0-10 numerical rating scale) and acceptable tolerability of XTAMPZA ER and entered the randomized, double-blind maintenance phase. Subjects discontinued from the dose-titration phase for the following reasons: failure to meet entrance criteria (18%), adverse events (13%), subject request (7%) and lack of efficacy (5%). Patients were randomized at a ratio of 1:1 into a 12-week double-blind maintenance phase with their fixed stable dose of XTAMPZA ER (or matching placebo). Patients randomized to placebo were given a blinded taper of XTAMPZA ER according to a prespecified tapering schedule; XTAMPZA ER was decreased by 25% to 35% every 5 days for the higher doses of XTAMPZA ER and up to 50% every 5 days for the mid-to-lower doses of XTAMPZA ER over the first 20 days of the double-blind maintenance phase. Patients were allowed to use rescue medication (acetaminophen 500 mg tablets) up to a maximum dose of 2000 mg per day. During the double-blind maintenance phase, 122 patients (63%) completed the 12-week treatment with XTAMPZA ER and 100 (51%) completed with placebo. Overall, 11% of patients discontinued due to lack of efficacy (4% of XTAMPZA ER patients and 17% of placebo patients), and 7% discontinued due to adverse events (7% of XTAMPZA ER patients and 7% of placebo patients).

In this study, there was a significant difference in pain reduction, favoring XTAMPZA ER, between XTAMPZA ER (doses of 36-144 mg per day, equivalent to 40-160 mg of oxycodone HCl) and placebo, based on the primary endpoint of change in average pain intensity from randomization baseline to Week 12 of the double-blind maintenance phase.

The proportion of patients (responders) in each group who demonstrated improvement in their weekly average pain scores from screening baseline to Week 12, is shown in Figure 2. The figure is cumulative, so that patients whose change from screening is, for example, 30%, are also included at every level of improvement below 30%. Patients who did not complete the study were classified as non-responders. Treatment with XTAMPZA ER resulted in a higher proportion of responders, defined as patients with at least a 30% and 50% improvement as compared to placebo.

Figure 2: Responder Analysis for Pain Intensity: Percent Reduction/Improvement (Intent-to-Treat Population)

16 HOW SUPPLIED/STORAGE AND HANDLING

XTAMPZA ER capsules are supplied in 100-count bottles with a child-resistant closure and as a hospital unit dose package with 10 individually blistered capsules per card; two cards per carton as follows:

Table 9: Summary of XTAMPZA ER Capsule Strengths and Packaging Configurations
Strength | Capsule Description | NDC Number (100-count Bottles with a child-resistant closure) | NDC Number (20-count Hospital Unit Dose Blister Cartons)
9 mg (equivalent to 10 mg oxycodone HCl) | Size 3, ivory cap printed with "XTAMPZA ER" and white body printed with "9 mg" | NDC 24510-110-10 | NDC 24510-110-20
13.5 mg (equivalent to 15 mg oxycodone HCl) | Size 2, Swedish orange cap printed with "XTAMPZA ER" and white body printed with "13.5 mg" | NDC 24510-115-10 | NDC 24510-115-20
18 mg (equivalent to 20 mg oxycodone HCl) | Size 1, rich yellow cap printed with "XTAMPZA ER" and white body printed with "18 mg" | NDC 24510-120-10 | NDC 24510-120-20
27 mg (equivalent to 30 mg oxycodone HCl) | Size 0, light gray cap printed with "XTAMPZA ER" and white body printed with "27 mg" | NDC 24510-130-10 | NDC 24510-130-20
36 mg (equivalent to 40 mg oxycodone HCl) | Size 00, flesh color cap printed with "XTAMPZA ER" and white body printed with "36 mg" | NDC 24510-140-10 | NDC 24510-140-20

STORAGE AND HANDLING

Store at 25°C (77°F); excursions permitted between 15°-30°C (59°-86°F) [see USP Controlled Room Temperature].

Dispense in tight, light-resistant container, with child-resistant closure.

Store XTAMPZA ER securely and dispose of properly [see Patient Counseling Information (17)].

17 PATIENT COUNSELING INFORMATION

Advise the patient to read the FDA-approved patient labeling (Medication Guide).

Storage and Disposal

Because of the risks associated with accidental ingestion, misuse, and abuse, advise patients to store XTAMPZA ER securely, out of sight and reach of children, and in a location not accessible by others, including visitors to the home. Inform patients that leaving XTAMPZA ER unsecured can pose a deadly risk to others in the home [see Warnings and Precautions (5.1, 5.2), Drug Abuse and Dependence (9.2)].

Advise patients and caregivers that when medicines are no longer needed, they should be disposed of promptly. Expired, unwanted, or unused XTAMPZA ER should be disposed of by flushing the unused medication down the toilet if a drug take-back option is not readily available. Inform patients that they can visit www.fda.gov/drugdisposal for a complete list of medicines recommended for disposal by flushing, as well as additional information on disposal of unused medicines.

Addiction, Abuse, and Misuse

Inform patients that the use of XTAMPZA ER, even when taken as recommended, can result in addiction, abuse, and misuse, which can lead to overdose and death [see Warnings and Precautions (5.1)]. Instruct patients not to share XTAMPZA ER with others and to take steps to protect XTAMPZA ER from theft or misuse.

Life-Threatening Respiratory Depression

Inform patients of the risk of life-threatening respiratory depression including information that the risk is greatest when starting XTAMPZA ER or when the dosage is increased, and that it can occur even at recommended dosages.

Educate patients and caregivers on how to recognize respiratory depression and emphasize the importance of calling 911 or getting emergency medical help right away in the event of a known or suspected overdose [see Warnings and Precautions (5.2)].

Accidental Ingestion

Inform patients that accidental ingestion, especially by children, may result in respiratory depression or death [see Warnings and Precautions (5.2)].

Interactions with Benzodiazepines and other CNS Depressants

Inform patients and caregivers that potentially fatal additive effects may occur if XTAMPZA ER is used with benzodiazepines or other CNS depressants, including alcohol (e.g., non-benzodiazepine sedative/hypnotics, anxiolytics, tranquilizers, muscle relaxants, general anesthetics, antipsychotics, gabapentinoids [gabapentin or pregabalin], and other opioids), and not to use these concomitantly unless supervised by a healthcare provider [see Warnings and Precautions (5.3), Drug Interactions (7)].

Patient Access to an Opioid Overdose Reversal Agent for the Emergency Treatment of Opioid Overdose

Inform patients and caregivers about opioid overdose reversal agents (e.g., naloxone, nalmefene). Discuss the importance of having access to an opioid overdose reversal agent, especially if the patient has risk factors for overdose (e.g., concomitant use of CNS depressants, a history of opioid use disorder, or prior opioid overdose) or if there are household members (including children) or other close contacts at risk for accidental ingestion or opioid overdose.

Discuss with the patient the options for obtaining an opioid overdose reversal agent (e.g., prescription, over-the-counter, or as part of a community-based program) [see Dosage and Administration (2.2), Warnings and Precautions (5.3)].

Educate patients and caregivers on how to recognize the signs and symptoms of an overdose.

Explain to patients and caregivers that effects of opioid overdose reversal agents like naloxone and nalmefene are temporary, and that they must call 911 or get emergency medical help right away in cases of known or suspected opioid overdose, even if an opioid overdose reversal agent is administered [see Overdosage (10)].

Advise patients and caregivers:

- how to treat with the overdose reversal agent in the event of an opioid overdose.
- to tell family and friends about the opioid overdose reversal agent, and to keep it in a place where family and friends can access it in an emergency.
- to read the Patient Information (or other educational material) that will come with their opioid overdose reversal agent. Emphasize the importance of doing this before an opioid emergency happens, so the patient and caregiver will know what to do.

Hyperalgesia and Allodynia

Inform patients and caregivers not to increase opioid dosage without first consulting a clinician. Advise patients to seek medical attention if they experience symptoms of hyperalgesia, including worsening pain, increased sensitivity to pain, or new pain [see Warnings and Precautions (5.7), Adverse Reactions (6.2)].

Serotonin Syndrome

Inform patients that XTAMPZA ER could cause a rare but potentially life-threatening condition called serotonin syndrome resulting from concomitant administration of serotonergic drugs. Warn patients of the symptoms of serotonin syndrome and to seek medical attention right away if symptoms develop. Instruct patients to inform their physicians if they are taking, or plan to take serotonergic medications. [see Drug Interactions (7)].

MAOI Interaction

Inform patients to avoid taking XTAMPZA ER while using any drugs that inhibit monoamine oxidase. Patients should not start MAOIs while taking XTAMPZA ER [see Drug Interactions (7)].

Food Effect

Because food has an effect on absorption of oxycodone from XTAMPZA ER, each dose of XTAMPZA ER should be taken with food in order to ensure that appropriate plasma levels are consistently achieved. Instruct patients to take XTAMPZA ER with approximately the same amount of food regardless of whether they swallow the capsule whole or sprinkle on soft food or into a cup and then administer directly into the mouth.

XTAMPZA ER may be taken as intact capsules or, alternately, may be administered as a sprinkle on soft foods or sprinkled into a cup and administered directly into the mouth, or through a nasogastric or gastric feeding tube [see Dosage and Administration (2.1,2.7)].

Important Administration Instructions [see Dosage and Administration (2.1, 2.6, 2.7), Warnings and Precautions (5.2)]

Instruct patients how to properly take XTAMPZA ER, including the following:

- Taking XTAMPZA ER with food
- Swallowing XTAMPZA ER capsules whole or sprinkling the capsule contents on soft food or into a cup and administering directly into the mouth
- Using XTAMPZA ER exactly as prescribed to reduce the risk of life-threatening adverse reactions (e.g., respiratory depression)

Important Discontinuation Instructions

In order to avoid developing withdrawal symptoms, instruct patients not to discontinue XTAMPZA ER without first discussing a tapering plan with the prescriber [see Dosage and Administration (2.6)]

Driving or Operating Heavy Machinery

Inform patients that XTAMPZA ER may impair the ability to perform potentially hazardous activities such as driving a car or operating heavy machinery. Advise patients not to perform such tasks until they know how they will react to the medication [see Warnings and Precautions (5.15)].

Constipation

Advise patients of the potential for severe constipation, including management instructions and when to seek medical attention.

Adrenal Insufficiency

Inform patients that XTAMPZA ER could cause adrenal insufficiency, a potentially life-threatening condition. Adrenal insufficiency may present with non-specific symptoms and signs such as nausea, vomiting, anorexia, fatigue, weakness, dizziness, and low blood pressure. Advise patients to seek medical attention if they experience a constellation of these symptoms [see Warnings and Precautions (5.9)].

Hypotension

Inform patients that XTAMPZA ER may cause orthostatic hypotension and syncope. Instruct patients how to recognize symptoms of low blood pressure and how to reduce the risk of serious consequences should hypotension occur (e.g., sit or lie down, carefully rise from a sitting or lying position) [see Warnings and Precautions (5.10)].

Anaphylaxis

Inform patients that anaphylaxis has been reported with ingredients contained in XTAMPZA ER. Advise patients how to recognize such a reaction and when to seek medical attention [see Contraindications (4), Adverse Reactions (6)].

Pregnancy

Neonatal Opioid Withdrawal Syndrome

Inform female patients of reproductive potential that use of XTAMPZA ER for an extended period of time during pregnancy can result in neonatal opioid withdrawal syndrome, which may be life-threatening if not recognized and treated [see Warnings and Precautions (5.4), Use in Specific Populations (8.1)].

Embryofetal Toxicity

Advise females of reproductive potential that XTAMPZA ER can cause fetal harm and to inform their healthcare provider of a known or suspected pregnancy [see Use in Specific Populations (8.1)].

Lactation

Advise patients that breastfeeding is not recommended during treatment with XTAMPZA ER [see Use in Specific Populations (8.2)].

Infertility

Inform patients that use of opioids for an extended period of time may cause reduced fertility. It is not known whether these effects on fertility are reversible [see Adverse Reactions (6.2)].

Healthcare professionals can telephone Collegium Pharmaceutical's Medical Affairs Department (1-855-331-5615) for information on this product.

Manufactured by: Patheon Pharmaceuticals, Cincinnati, OH 45237

U.S. Patent Nos. 7,399,488; 7,771,707; 8,449,909; 8,557,291; 8,758,813; 8,840,928; 9,044,398; 9,248,195; 9,592,200; 9,682,075; 9,737,530; 9,763,883; 9,968,598; 10,004,729; 10,188,644; 10,525,052; 10,525,053; 10,646,485; and 10,668,060

Medication Guide
XTAMPZA® ER (ex tamp' zah ee ar)
(oxycodone) extended-release capsules, CII

XTAMPZA ER is:

- A strong prescription pain medicine that contains an opioid (narcotic) that is used to manage severe and persistent pain that requires an extended treatment period with a daily opioid medicine, when other pain medicines do not treat your pain well enough or you cannot tolerate them.
- A long-acting (extended-release) opioid pain medicine that can put you at risk for overdose and death. Even if you take your dose correctly as prescribed by your healthcare provider, you are at risk for opioid addiction, abuse, and misuse that can lead to death.
- Not to be taken on an "as needed" basis

Important information about XTAMPZA ER:

- Get emergency help or call 911 right away if you take too much XTAMPZA ER (overdose). When you first start taking XTAMPZA ER, when your dose is changed, or if you take too much (overdose), serious life-threatening breathing problems that can lead to death may occur. Ask your healthcare provider about medicines like naloxone or nalmefene that can be used in an emergency to reverse an opioid overdose.
- Taking XTAMPZA ER with other opioid medicines, benzodiazepines, gabapentinoids (gabapentin or pregabalin), alcohol, or other central nervous system depressants (including street drugs) can cause severe drowsiness, decreased awareness, breathing problems, coma, and death.
- Never give anyone else your XTAMPZA ER. They could die from taking it. Selling or giving away XTAMPZA ER is against the law.
- Store XTAMPZA ER securely, out of sight and reach of children, and in a location not accessible by others, including visitors to the home.

Do not take XTAMPZA ER if you have:

- severe asthma, trouble breathing, or other lung problems.
- a bowel blockage or have narrowing of the stomach or intestines.

Before taking XTAMPZA ER, tell your healthcare provider if you have a history of:

- head injury, seizures
- problems urinating

- liver, kidney, thyroid problems
- pancreas or gallbladder problems

- abuse of street or prescription drugs, alcohol addiction, opioid overdose, or mental health problems.

Tell your healthcare provider if you are:

- noticing your pain getting worse. If your pain gets worse after you take XTAMPZA ER, do not take more of XTAMPZA ER without first talking to your healthcare provider. Talk to your healthcare provider if the pain that you have increases, if you feel more sensitive to pain, or if you have new pain after taking XTAMPZA ER.
- pregnant or planning to become pregnant. Use of XTAMPZA ER for an extended period of time during pregnancy can cause withdrawal symptoms in your newborn baby that could be life-threatening if not recognized and treated.
- breastfeeding. Not recommended during treatment with XTAMPZA ER. It may harm your baby.
- living in a household where there are small children or someone who has abused street or prescription drugs
- taking prescription or over-the-counter medicines, vitamins, or herbal supplements. Taking XTAMPZA ER with certain other medicines can cause serious side effects that could lead to death.

When taking XTAMPZA ER:

- Do not change your dose. Take XTAMPZA ER exactly as prescribed by your healthcare provider. Use the lowest dose possible for the shortest time needed.
- Take your prescribed dose every 12 hours, at the same time every day. Do not take more than your prescribed dose. If you miss a dose, take your next dose at your usual time.
- If you cannot swallow XTAMPZA ER capsules, see the detailed Instructions for Use.
- Always take XTAMPZA ER capsules with approximately the same amount of food to ensure enough medicine is absorbed.
- Swallow XTAMPZA ER whole. Do not snort or inject XTAMPZA ER because this may cause you to overdose and die.
- The contents of the XTAMPZA ER capsules may be sprinkled on soft food, sprinkled into a cup and then put directly into the mouth, or given through a nasogastric or gastrostomy tube.
- Call your healthcare provider if the dose you are taking does not control your pain.
- Do not stop taking XTAMPZA ER without talking to your healthcare provider.
- Dispose of expired, unwanted, or unused XTAMPZA ER by promptly flushing down the toilet, if a drug take-back option is not readily available. Visit www.fda.gov/drugdisposal for additional information on disposal of unused medicines.

While taking XTAMPZA ER DO NOT:

- Drive or operate heavy machinery, until you know how XTAMPZA ER affects you. XTAMPZA ER can make you sleepy, dizzy, or lightheaded.
- Drink alcohol or use prescription or over-the-counter medicines that contain alcohol. Using products containing alcohol during treatment with XTAMPZA ER may cause you to overdose and die.

The possible side effects of XTAMPZA ER are:

- constipation, nausea, sleepiness, vomiting, tiredness, headache, dizziness, abdominal pain. Call your healthcare provider if you have any of these symptoms and they are severe.

Get emergency medical help or call 911 right away if you have:

- trouble breathing, shortness of breath, fast heartbeat, chest pain, swelling of your face, tongue, or throat, extreme drowsiness, light-headedness when changing positions, feeling faint, agitation, high body temperature, trouble walking, stiff muscles, or mental changes such as confusion.

These are not all the possible side effects of XTAMPZA ER. Call your healthcare provider for medical advice about side effects. You may report side effects to the FDA at 1-800-FDA-1088. For more information, go to dailymed.nlm.nih.gov
Manufactured by: Patheon Pharmaceuticals, 2110 Galbraith Road, Cincinnati, OH 45237, www.collegiumpharma.com or call 855-331-5615

This Medication Guide has been approved by the U.S. Food and Drug Administration.

Issued: December 2025

Instructions for Use XTAMPZA® ER (ex tamp' zah ee ar) (oxycodone) extended-release capsules, CII

Always take XTAMPZA ER with approximately the same amount of food. If you cannot swallow XTAMPZA ER capsules, tell your healthcare provider. If your healthcare provider tells you that you can take XTAMPZA ER by sprinkling the capsule contents, follow these steps:

XTAMPZA ER can be opened and the contents inside the capsule can be sprinkled onto soft foods (such as, applesauce, pudding, yogurt, ice cream, or jam) as follows:

Figure 1

- Open the XTAMPZA ER capsule and sprinkle the contents over about one tablespoon of the soft food listed above (See Figure 1).

Figure 2

- Swallow all of the soft food and sprinkled capsule contents right away. Do not save any of the soft food and capsule contents for another dose (See Figure 2).

Figure 3

- Rinse your mouth to make sure you have swallowed all of the capsule contents. (See Figure 3).

Figure 4

- Flush the empty capsule down the toilet right away (See Figure 4).

XTAMPZA ER capsule contents can also be sprinkled into a cup and then put directly into the mouth.

Giving XTAMPZA ER through a nasogastric or gastrostomy tube:
Use water, milk, or a liquid nutritional supplement to flush the tube when giving XTAMPZA ER.

Step 1: | Flush the nasogastric or gastrostomy tube with liquid.
Step 2: | Open an XTAMPZA ER capsule and carefully pour the contents of the capsule directly into the tube. Do not pre-mix the capsule contents with the liquid used to flush the capsule contents through the tube.
Step 3: | Draw up 15 mL of liquid into a syringe, insert the syringe into the tube, and flush the contents of the capsule through the tube to give the dose.
Step 4: | Flush the tube two more times, each time with 10 mL of liquid, to ensure that none of the contents of the capsule are left in the tube.

This Instruction for Use has been approved by the U.S. Food and Drug Administration. Issued: December 2025

Collegium®
PHARMACEUTICAL

PRINCIPAL DISPLAY PANEL - 9 mg Capsule Bottle Label

NDC 24510-110-10

Xtampza® ER

(oxycodone)
EXTENDED-RELEASE
CAPSULES
CII

9 mg

Each capsule contains Oxycodone 9 mg
(Equivalent to 10 mg Oxycodone Hydrochloride)

100 Capsules
Rx Only

Always take with food. Taking on an empty
stomach can decrease drug absorption.

Attention Dispenser: Accompanying Medication
Guide must be provided to the patient upon dispensing.

PRINCIPAL DISPLAY PANEL - 13.5 mg Capsule Bottle Label

NDC 24510-115-10

Xtampza® ER

(oxycodone)
EXTENDED-RELEASE
CAPSULES
CII

13.5 mg

Each capsule contains Oxycodone 13.5 mg
(Equivalent to 15 mg Oxycodone Hydrochloride)

100 Capsules
Rx Only

Always take with food. Taking on an empty
stomach can decrease drug absorption.

Attention Dispenser: Accompanying
Medication Guide must be provided to
the patient upon dispensing.

PRINCIPAL DISPLAY PANEL - 18 mg Capsule Bottle Label

NDC 24510-120-10

Xtampza® ER

(oxycodone)
EXTENDED-RELEASE
CAPSULES
CII

18 mg

Each capsule contains Oxycodone 18 mg
(Equivalent to 20 mg Oxycodone Hydrochloride)

100 Capsules
Rx Only

Always take with food. Taking on an empty
stomach can decrease drug absorption.

Attention Dispenser: Accompanying
Medication Guide must be provided to
the patient upon dispensing.

PRINCIPAL DISPLAY PANEL - 27 mg Capsule Bottle Label

NDC 24510-130-10

Xtampza® ER

(oxycodone)
EXTENDED-RELEASE
CAPSULES
CII

27 mg

Each capsule contains Oxycodone 27 mg
(Equivalent to 30 mg Oxycodone Hydrochloride)

100 Capsules
Rx Only

Always take with food. Taking on an empty
stomach can decrease drug absorption.

Attention Dispenser: Accompanying
Medication Guide must be provided to
the patient upon dispensing.

PRINCIPAL DISPLAY PANEL - 36 mg Capsule Bottle Label

NDC 24510-140-10

Xtampza® ER

(oxycodone)
EXTENDED-RELEASE
CAPSULES
CII

36 mg

Each capsule contains Oxycodone 36 mg
(Equivalent to 40 mg Oxycodone Hydrochloride)

100 Capsules
Rx Only

Always take with food. Taking on an empty
stomach can decrease drug absorption.

Attention Dispenser: Accompanying
Medication Guide must be provided to
the patient upon dispensing.